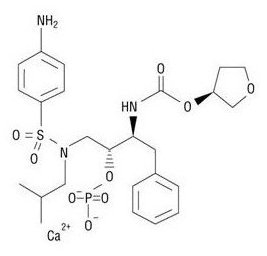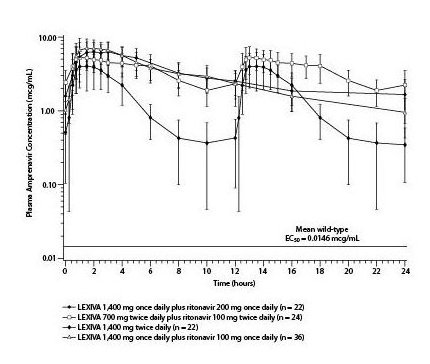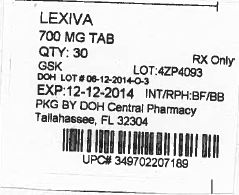 DRUG LABEL: LEXIVA
NDC: 53808-1010 | Form: TABLET, FILM COATED
Manufacturer: State of Florida DOH Central Pharmacy
Category: prescription | Type: HUMAN PRESCRIPTION DRUG LABEL
Date: 20150110

ACTIVE INGREDIENTS: FOSAMPRENAVIR CALCIUM 700 mg/1 1
INACTIVE INGREDIENTS: COLLOIDAL SILICON DIOXIDE; CROSCARMELLOSE SODIUM; MAGNESIUM STEARATE; CELLULOSE, MICROCRYSTALLINE; POVIDONE K30; HYPROMELLOSES; FERRIC OXIDE RED; TITANIUM DIOXIDE; TRIACETIN

HIGHLIGHTS OF PRESCRIBING INFORMATION

These highlights do not include all the information needed to use LEXIVA safely and effectively. See full prescribing information for LEXIVA.
LEXIVA (fosamprenavir calcium) Tablets, for oral use
LEXIVA (fosamprenavir calcium) Oral Suspension
Initial U.S. Approval: 2003

1 INDICATIONS AND USAGE

LEXIVA is an HIV protease inhibitor indicated in combination with other antiretroviral agents for the treatment of HIV-1 infection. (1)

2 DOSAGE AND ADMINISTRATION

- Therapy-Naive Adults: LEXIVA 1,400 mg twice daily; LEXIVA 1,400 mg once daily plus ritonavir 200 mg once daily; LEXIVA 1,400 mg once daily plus ritonavir 100 mg once daily; LEXIVA 700 mg twice daily plus ritonavir 100 mg twice daily. (2.1)
- Protease Inhibitor-Experienced Adults: LEXIVA 700 mg twice daily plus ritonavir 100 mg twice daily. (2.1)
- Pediatric Patients (aged at least 4 weeks to 18 years): Dosage should be calculated based on body weight (kg) and should not exceed adult dose. (2.2)
- Hepatic Impairment: Recommended adjustments for patients with mild, moderate, or severe hepatic impairment. (2.3)

Dosing Considerations

- LEXIVA Tablets may be taken with or without food. (2)
- LEXIVA Suspension: Adults should take without food; pediatric patients should take with food. (2)

3 DOSAGE FORMS AND STRENGTHS

700 mg tablets and 50 mg per mL oral suspension (3)

4 CONTRAINDICATIONS

- Hypersensitivity to LEXIVA or amprenavir (e.g., Stevens-Johnson syndrome). (4)
- Drugs highly dependent on CYP3A4 for clearance and for which elevated plasma levels may result in serious and/or life-threatening events. (4)
- Review ritonavir contraindications when used in combination. (4)

WARNINGS AND PRECAUTIONS

- Certain drugs should not be coadministered with LEXIVA due to risk of serious or life-threatening adverse reactions. (5.1)
- LEXIVA should be discontinued for severe skin reactions including Stevens-Johnson syndrome. (5.2)
- LEXIVA should be used with caution in patients with a known sulfonamide allergy. (5.3)
- Use of higher than approved doses may lead to transaminase elevations. Patients with hepatitis B or C are at increased risk of transaminase elevations. (5.4)
- Patients receiving LEXIVA may develop new onset or exacerbations of diabetes mellitus, hyperglycemia (5.5), immune reconstitution syndrome (5.6), redistribution/accumulation of body fat (5.7), and elevated triglyceride and cholesterol concentrations (5.8). Monitor cholesterol and triglycerides prior to therapy and periodically thereafter.
- Acute hemolytic anemia has been reported with amprenavir. (5.9)
- Hemophilia: Spontaneous bleeding may occur, and additional factor VIII may be required. (5.10)
- Nephrolithiasis: Cases of nephrolithiasis have been reported with fosamprenavir. (5.11)

6 ADVERSE REACTIONS

- In adults the most common adverse reactions (incidence greater than or equal to 4%) are diarrhea, rash, nausea, vomiting, headache. (6.1)
- Vomiting and neutropenia were more frequent in pediatrics than in adults. (6.1)

To report SUSPECTED ADVERSE REACTIONS, contact ViiV Healthcare at 1-877-844-8872 or FDA at 1-800-FDA-1088 or www.fda.gov/medwatch.

7 DRUG INTERACTIONS

- Coadministration of LEXIVA with drugs that induce CYP3A4 may decrease amprenavir (active metabolite) concentrations leading to potential loss of virologic activity. (7, 12.3)
- Coadministration with drugs that inhibit CYP3A4 may increase amprenavir concentrations. (7, 12.3)
- Coadministration of LEXIVA and ritonavir may result in clinically significant interactions with drugs metabolized by CYP2D6. (7)

FULL PRESCRIBING INFORMATION

1 INDICATIONS AND USAGE

LEXIVA® is indicated in combination with other antiretroviral agents for the treatment of human immunodeficiency virus (HIV-1) infection.

The following points should be considered when initiating therapy with LEXIVA plus ritonavir in protease inhibitor-experienced patients:

- The protease inhibitor-experienced patient trial was not large enough to reach a definitive conclusion that LEXIVA plus ritonavir and lopinavir plus ritonavir are clinically equivalent [see Clinical Studies (14.2)].
- Once-daily administration of LEXIVA plus ritonavir is not recommended for adult protease inhibitor-experienced patients or any pediatric patients [see Dosage and Administration (2.1, 2.2), Clinical Studies (14.2, 14.3)].
- Dosing of LEXIVA plus ritonavir is not recommended for protease inhibitor-experienced pediatric patients younger than 6 months [see Clinical Pharmacology (12.3)].

2 DOSAGE AND ADMINISTRATION

LEXIVA Tablets may be taken with or without food.

Adults should take LEXIVA Oral Suspension without food. Pediatric patients should take LEXIVA Oral Suspension with food [see Clinical Pharmacology (12.3)]. If emesis occurs within 30 minutes after dosing, re-dosing of LEXIVA Oral Suspension should occur.

Higher-than-approved dose combinations of LEXIVA plus ritonavir are not recommended due to an increased risk of transaminase elevations [see Overdosage (10)].

When LEXIVA is used in combination with ritonavir, prescribers should consult the full prescribing information for ritonavir.

2.1 Adults

Therapy-Naive Adults:

- LEXIVA 1,400 mg twice daily (without ritonavir).
- LEXIVA 1,400 mg once daily plus ritonavir 200 mg once daily.
- LEXIVA 1,400 mg once daily plus ritonavir 100 mg once daily.
  ∘ Dosing of LEXIVA 1,400 mg once daily plus ritonavir 100 mg once daily is supported by pharmacokinetic data [see Clinical Pharmacology (12.3)].
- LEXIVA 700 mg twice daily plus ritonavir 100 mg twice daily.
  ∘ Dosing of LEXIVA 700 mg twice daily plus 100 mg ritonavir twice daily is supported by pharmacokinetic and safety data [see Clinical Pharmacology (12.3)].

Protease Inhibitor-Experienced Adults:

- LEXIVA 700 mg twice daily plus ritonavir 100 mg twice daily.

2.2 Pediatric Patients (Aged at Least 4 Weeks to 18 Years)

The recommended dosage of LEXIVA in patients aged at least 4 weeks to 18 years should be calculated based on body weight (kg) and should not exceed the recommended adult dose (Table 1).

Table 1. Twice-Daily Dosage Regimens by Weight for Protease Inhibitor-Naive Pediatric Patients (Greater Than or Equal to 4 Weeks of Age) and for Protease Inhibitor-Experienced Pediatric Patients (Greater Than or Equal to 6 Months of Age) Using LEXIVA Oral Suspension With Concurrent Ritonavir

Weight | Twice-Daily Dosage Regimen
<11 kg | LEXIVA 45 mg/kg plus ritonavir 7 mg/kga
11 kg - <15 kg | LEXIVA 30 mg/kg plus ritonavir 3 mg/kga
15 kg - <20 kg | LEXIVA 23 mg/kg plus ritonavir 3 mg/kga
≥20 kg | LEXIVA 18 mg/kg plus ritonavir 3 mg/kga

aWhen dosing with ritonavir, do not exceed the adult dose of LEXIVA 700 mg/
ritonavir 100 mg twice-daily dose.

Alternatively, protease inhibitor-naive children aged 2 years and older can be administered LEXIVA (without ritonavir) 30 mg per kg twice daily.

LEXIVA should only be administered to infants born at 38 weeks gestation or greater and who have attained a post-natal age of 28 days.

For pediatric patients, pharmacokinetic and clinical data:

- do not support once-daily dosing of LEXIVA alone or in combination with ritonavir [see Clinical Studies (14.3)].
- do not support administration of LEXIVA alone or in combination with ritonavir for protease inhibitor‑experienced children younger than 6 months [see Clinical Pharmacology (12.3)].
- do not support twice-daily dosing of LEXIVA without ritonavir in pediatric patients younger than 2 years [see Clinical Pharmacology (12.3)].

Other Dosing Considerations:

- When administered without ritonavir, the adult regimen of LEXIVA Tablets 1,400 mg twice daily may be used for pediatric patients weighing at least 47 kg.
- When administered in combination with ritonavir, LEXIVA Tablets may be used for pediatric patients weighing at least 39 kg; ritonavir capsules may be used for pediatric patients weighing at least 33 kg.

2.3 Patients With Hepatic Impairment

See Clinical Pharmacology (12.3).

Mild Hepatic Impairment (Child-Pugh Score Ranging From 5 to 6): LEXIVA should be used with caution at a reduced dosage of 700 mg twice daily without ritonavir (therapy-naive) or 700 mg twice daily plus ritonavir 100 mg once daily (therapy-naive or protease inhibitor-experienced).

Moderate Hepatic Impairment (Child-Pugh Score Ranging From 7 to 9): LEXIVA should be used with caution at a reduced dosage of 700 mg twice daily without ritonavir (therapy-naive), or 450 mg twice daily plus ritonavir 100 mg once daily (therapy-naive or protease inhibitor-experienced).

Severe Hepatic Impairment (Child-Pugh Score Ranging From 10 to 15): LEXIVA should be used with caution at a reduced dosage of 350 mg twice daily without ritonavir (therapy-naive) or 300 mg twice daily plus ritonavir 100 mg once daily (therapy-naive or protease inhibitor-experienced).

There are no data to support dosing recommendations for pediatric patients with hepatic impairment.

3 DOSAGE FORMS AND STRENGTHS

LEXIVA Tablets, 700 mg, are pink, film-coated, capsule-shaped, biconvex tablets with “GX LL7” debossed on one face.

LEXIVA Oral Suspension, 50 mg per mL, is a white to off-white suspension that has a characteristic grape-bubblegum-peppermint flavor.

4 CONTRAINDICATIONS

LEXIVA is contraindicated:

- in patients with previously demonstrated clinically significant hypersensitivity (e.g., Stevens-Johnson syndrome) to any of the components of this product or to amprenavir.
- when coadministered with drugs that are highly dependent on cytochrome P450 3A4 (CYP3A4) for clearance and for which elevated plasma concentrations are associated with serious and/or life-threatening events (Table 2).

Table 2. Drugs Contraindicated With LEXIVA. (Information in the table applies to LEXIVA with or without ritonavir, unless otherwise indicated.)
Drug Class/Drug Name | Clinical Comment
Alpha 1-adrenoreceptor antagonist:; Alfuzosin | Potentially increased alfuzosin concentrations can result in hypotension.
Antiarrhythmics:; Flecainide, propafenone | POTENTIAL for serious and/or life-threatening reactions such as cardiac arrhythmias secondary to increases in plasma concentrations of antiarrhythmics if LEXIVA is co-prescribed with ritonavir.
Antimycobacterials:; Rifampina | May lead to loss of virologic response and possible resistance to LEXIVA or to the class of protease inhibitors.
Ergot derivatives:; Dihydroergotamine, ergonovine, ergotamine, methylergonovine | POTENTIAL for serious and/or life-threatening reactions such as acute ergot toxicity characterized by peripheral vasospasm and ischemia of the extremities and other tissues.
GI motility agents:; Cisapride | POTENTIAL for serious and/or life-threatening reactions such as cardiac arrhythmias.
Herbal products:; St. John’s wort (Hypericum perforatum) | May lead to loss of virologic response and possible resistance to LEXIVA or to the class of protease inhibitors.
HMG co-reductase inhibitors:; Lovastatin, simvastatin | POTENTIAL for serious reactions such as risk of myopathy including rhabdomyolysis.
Neuroleptic:; Pimozide | POTENTIAL for serious and/or life-threatening reactions such as cardiac arrhythmias.
Non-nucleoside reverse transcriptase inhibitor:; Delavirdinea | May lead to loss of virologic response and possible resistance to delavirdine.
PDE5 inhibitor:; Sildenafil (REVATIO®) (for treatment of pulmonary arterial hypertension) | A safe and effective dose has not been established when used with LEXIVA. There is increased potential for sildenafil-associated adverse events (which include visual disturbances, hypotension, prolonged erection, and syncope).
Sedative/hypnotics:; Midazolam, triazolam | POTENTIAL for serious and/or life-threatening reactions such as prolonged or increased sedation or respiratory depression.

a See Clinical Pharmacology (12.3) Tables 10, 11, 12, or 13 for magnitude of interaction.

- when coadministered with ritonavir in patients receiving the antiarrhythmic agents, flecainide and propafenone. If LEXIVA is coadministered with ritonavir, reference should be made to the full prescribing information for ritonavir for additional contraindications.

WARNINGS AND PRECAUTIONS

5.1 Drug Interactions

See Table 2 for listings of drugs that are contraindicated due to potentially life-threatening adverse events, significant drug interactions, or loss of virologic activity [see Contraindications (4), Drug Interactions (7.2)]. See Table 7 for a listing of established and other potentially significant drug interactions [see Drug Interactions (7.3)].

5.2 Skin Reactions

Severe and life-threatening skin reactions, including 1 case of Stevens-Johnson syndrome among 700 subjects treated with LEXIVA in clinical trials. Treatment with LEXIVA should be discontinued for severe or life-threatening rashes and for moderate rashes accompanied by systemic symptoms [see Adverse Reactions (6)].

5.3 Sulfa Allergy

LEXIVA should be used with caution in patients with a known sulfonamide allergy. Fosamprenavir contains a sulfonamide moiety. The potential for cross-sensitivity between drugs in the sulfonamide class and fosamprenavir is unknown. In a clinical trial of LEXIVA used as the sole protease inhibitor, rash occurred in 2 of 10 subjects (20%) with a history of sulfonamide allergy compared with 42 of 126 subjects (33%) with no history of sulfonamide allergy. In 2 clinical trials of LEXIVA plus low-dose ritonavir, rash occurred in 8 of 50 subjects (16%) with a history of sulfonamide allergy compared with 50 of 412 subjects (12%) with no history of sulfonamide allergy.

5.4 Hepatic Toxicity

Use of LEXIVA with ritonavir at higher-than-recommended dosages may result in transaminase elevations and should not be used [see Dosage and Administration (2), Overdosage (10)]. Patients with underlying hepatitis B or C or marked elevations in transaminases prior to treatment may be at increased risk for developing or worsening of transaminase elevations. Appropriate laboratory testing should be conducted prior to initiating therapy with LEXIVA and patients should be monitored closely during treatment.

5.5 Diabetes/Hyperglycemia

New onset diabetes mellitus, exacerbation of pre-existing diabetes mellitus, and hyperglycemia have been reported during postmarketing surveillance in HIV-1-infected patients receiving protease inhibitor therapy. Some patients required either initiation or dose adjustments of insulin or oral hypoglycemic agents for treatment of these events. In some cases, diabetic ketoacidosis has occurred. In those patients who discontinued protease inhibitor therapy, hyperglycemia persisted in some cases. Because these events have been reported voluntarily during clinical practice, estimates of frequency cannot be made and causal relationships between protease inhibitor therapy and these events have not been established.

5.6 Immune Reconstitution Syndrome

Immune reconstitution syndrome has been reported in patients treated with combination antiretroviral therapy, including LEXIVA. During the initial phase of combination antiretroviral treatment, patients whose immune systems respond may develop an inflammatory response to indolent or residual opportunistic infections (such as Mycobacterium avium infection, cytomegalovirus, Pneumocystis jirovecii pneumonia [PCP], or tuberculosis), which may necessitate further evaluation and treatment.

Autoimmune disorders (such as Graves’ disease, polymyositis, and Guillain-Barré syndrome) have also been reported to occur in the setting of immune reconstitution; however, the time to onset is more variable, and can occur many months after initiation of treatment.

5.7 Fat Redistribution

Redistribution/accumulation of body fat, including central obesity, dorsocervical fat enlargement (buffalo hump), peripheral wasting, facial wasting, breast enlargement, and “cushingoid appearance,” have been observed in patients receiving antiretroviral therapy, including LEXIVA. The mechanism and long-term consequences of these events are currently unknown. A causal relationship has not been established.

5.8 Lipid Elevations

Treatment with LEXIVA plus ritonavir has resulted in increases in the concentration of triglycerides and cholesterol [see Adverse Reactions (6)]. Triglyceride and cholesterol testing should be performed prior to initiating therapy with LEXIVA and at periodic intervals during therapy. Lipid disorders should be managed as clinically appropriate [see Drug Interactions (7)].

5.9 Hemolytic Anemia

Acute hemolytic anemia has been reported in a patient treated with amprenavir.

5.10 Patients With Hemophilia

There have been reports of spontaneous bleeding in patients with hemophilia A and B treated with protease inhibitors. In some patients, additional factor VIII was required. In many of the reported cases, treatment with protease inhibitors was continued or restarted. A causal relationship between protease inhibitor therapy and these episodes has not been established.

5.11 Nephrolithiasis

Cases of nephrolithiasis were reported during postmarketing surveillance in HIV-1-infected patients receiving LEXIVA.Because these events were reported voluntarily during clinical practice, estimates of frequency cannot be made. If signs or symptoms of nephrolithiasis occur, temporary interruption or discontinuation of therapy may be considered.

5.12 Resistance/Cross-Resistance

Because the potential for HIV cross-resistance among protease inhibitors has not been fully explored, it is unknown what effect therapy with LEXIVA will have on the activity of subsequently administered protease inhibitors. LEXIVA has been studied in patients who have experienced treatment failure with protease inhibitors [see Clinical Studies (14.2)].

6 ADVERSE REACTIONS

- Severe or life-threatening skin reactions have been reported with the use of LEXIVA [see Warnings and Precautions (5.2)].
- The most common moderate to severe adverse reactions in clinical trials of LEXIVA were diarrhea, rash, nausea, vomiting, and headache.
- Treatment discontinuation due to adverse events occurred in 6.4% of subjects receiving LEXIVA and in 5.9% of subjects receiving comparator treatments. The most common adverse reactions leading to discontinuation of LEXIVA (incidence less than or equal to 1% of subjects) included diarrhea, nausea, vomiting, AST increased, ALT increased, and rash.

6.1 Clinical Trials

Because clinical trials are conducted under widely varying conditions, adverse reaction rates observed in the clinical trials of a drug cannot be directly compared to rates in the clinical trials of another drug and may not reflect the rates observed in clinical practice.

Adult Trials: The data for the 3 active-controlled clinical trials described below reflect exposure of 700 HIV-1–infected subjects to LEXIVA Tablets, including 599 subjects exposed to LEXIVA for greater than 24 weeks, and 409 subjects exposed for greater than 48 weeks. The population age ranged from 17 to 72 years. Of these subjects, 26% were female, 51% Caucasian, 31% black, 16% American Hispanic, and 70% were antiretroviral-naive. Sixty-one percent received LEXIVA 1,400 mg once daily plus ritonavir 200 mg once daily; 24% received LEXIVA 1,400 mg twice daily; and 15% received LEXIVA 700 mg twice daily plus ritonavir 100 mg twice daily.

Selected adverse reactions reported during the clinical efficacy trials of LEXIVA are shown in Tables 3 and 4. Each table presents adverse reactions of moderate or severe intensity in subjects treated with combination therapy for up to 48 weeks.

Table 3. Selected Moderate/Severe Clinical Adverse Reactions Reported in Greater Than or Equal to 2% of Antiretroviral-Naive Adult Subjects

Adverse Reaction | APV30001a |  | APV30002a
Adverse Reaction | LEXIVA; 1,400 mg b.i.d.; (n = 166) | Nelfinavir; 1,250 mg b.i.d.; (n = 83) | LEXIVA; 1,400 mg q.d./; Ritonavir; 200 mg q.d.; (n = 322) | Nelfinavir; 1,250 mg b.i.d.; (n = 327)
Gastrointestinal
Diarrhea | 5% | 18% | 10% | 18%
Nausea | 7% | 4% | 7% | 5%
Vomiting | 2% | 4% | 6% | 4%
Abdominal pain | 1% | 0% | 2% | 2%
Skin
Rash | 8% | 2% | 3% | 2%
General disorders
Fatigue | 2% | 1% | 4% | 2%
Nervous system
Headache | 2% | 4% | 3% | 3%

aAll subjects also received abacavir and lamivudine twice daily.

Table 4. Selected Moderate/Severe Clinical Adverse Reactions Reported in Greater Than or Equal to 2% of Protease Inhibitor-Experienced Adult Subjects (Trial APV30003)
Adverse Reaction | LEXIVA 700 mg b.i.d./; Ritonavir 100 mg b.i.d.a; (n = 106) | Lopinavir 400 mg b.i.d./; Ritonavir 100 mg b.i.d.a; (n = 103)
Gastrointestinal
Diarrhea | 13% | 11%
Nausea | 3% | 9%
Vomiting | 3% | 5%
Abdominal pain | <1% | 2%
Skin
Rash | 3% | 0%
Nervous system
Headache | 4% | 2%

aAll subjects also received 2 reverse transcriptase inhibitors.

Skin rash (without regard to causality) occurred in approximately 19% of subjects treated with LEXIVA in the pivotal efficacy trials. Rashes were usually maculopapular and of mild or moderate intensity, some with pruritus. Rash had a median onset of 11 days after initiation of LEXIVA and had a median duration of 13 days. Skin rash led to discontinuation of LEXIVA in less than 1% of subjects. In some subjects with mild or moderate rash, dosing with LEXIVA was often continued without interruption; if interrupted, reintroduction of LEXIVA generally did not result in rash recurrence.

The percentages of subjects with Grade 3 or 4 laboratory abnormalities in the clinical efficacy trials of LEXIVA are presented in Tables 5 and 6.

Table 5. Grade 3/4 Laboratory Abnormalities Reported in Greater Than or Equal to 2% of Antiretroviral-Naive Adult Subjects in Trials APV30001 and APV30002

Laboratory Abnormality | APV30001a |  | APV30002a
Laboratory Abnormality | LEXIVA; 1,400 mg b.i.d.; (n = 166) | Nelfinavir; 1,250 mg b.i.d.; (n = 83) | LEXIVA; 1,400 mg q.d./; Ritonavir; 200 mg q.d.; (n = 322) | Nelfinavir; 1,250 mg b.i.d.; (n = 327)
ALT (>5 x ULN) | 6% | 5% | 8% | 8%
AST (>5 x ULN) | 6% | 6% | 6% | 7%
Serum lipase (>2 x ULN) | 8% | 4% | 6% | 4%
Triglyceridesb (>750 mg/dL) | 0% | 1% | 6% | 2%
Neutrophil count, absolute (<750 cells/mm^3) | 3% | 6% | 3% | 4%

aAll subjects also received abacavir and lamivudine twice daily.

bFasting specimens.

ULN = Upper limit of normal.

The incidence of Grade 3 or 4 hyperglycemia in antiretroviral-naive subjects who received LEXIVA in the pivotal trials was less than 1%.

Table 6. Grade 3/4 Laboratory Abnormalities Reported in Greater Than or Equal to 2% of Protease Inhibitor-Experienced Adult Subjects in Trial APV30003

Laboratory Abnormality | LEXIVA 700 mg b.i.d./; Ritonavir 100 mg b.i.d.a; (n = 104) | Lopinavir 400 mg b.i.d./; Ritonavir 100 mg b.i.d.a; (n = 103)
Triglyceridesb (>750 mg/dL) | 11%c | 6%c
Serum lipase (>2 x ULN) | 5% | 12%
ALT (>5 x ULN) | 4% | 4%
AST (>5 x ULN) | 4% | 2%
Glucose (>251 mg/dL) | 2%c | 2%c

aAll subjects also received 2 reverse transcriptase inhibitors.

bFasting specimens.

cn = 100 for LEXIVA plus ritonavir, n = 98 for lopinavir plus ritonavir.

ULN = Upper limit of normal.

Pediatric Trials: LEXIVA with and without ritonavir was studied in 237 HIV-1–infected pediatric subjects aged at least 4 weeks to 18 years in 3 open‑label trials, APV20002, APV20003, and APV29005 [see Clinical Studies (14.3)]. Vomiting and neutropenia occurred more frequently in pediatric subjects compared to adults. Other adverse events occurred with similar frequency in pediatric subjects compared with adults.

The frequency of vomiting among pediatric subjects receiving LEXIVA twice daily with ritonavir was 20% in subjects aged at least 4 weeks to less than 2 years and 36% in subjects aged 2 to 18 years compared with 10% in adults. The frequency of vomiting among pediatric subjects receiving LEXIVA twice daily without ritonavir was 60% in subjects aged 2 to 5 years compared with 16% in adults.

The median duration of drug‑related vomiting episodes in APV29005 was 1 day (range: 1 to 3 days), in APV20003 was 16 days (range: 1 to 38 days), and in APV20002 was 9 days (range: 4 to 13 days). Vomiting was treatment limiting in 4 pediatric subjects across all 3 trials.

The incidence of Grade 3 or 4 neutropenia (neutrophils less than 750 cells per mm^3) seen in pediatric subjects treated with LEXIVA with and without ritonavir was higher (15%) than the incidence seen in adult subjects (3%). Grade 3/4 neutropenia occurred in 10% (5/51) of subjects aged at least 4 weeks to less than 2 years and 16% (28/170) of subjects aged 2 to 18 years.

6.2 Postmarketing Experience

In addition to adverse reactions reported from clinical trials, the following reactions have been identified during post-approval use of LEXIVA. Because they are reported voluntarily from a population of unknown size, estimates of frequency cannot be made. These reactions have been chosen for inclusion due to a combination of their seriousness, frequency of reporting, or potential causal connection to LEXIVA.

Cardiac Disorders: Myocardial infarction.

Metabolism and Nutrition Disorders: Hypercholesterolemia.

Nervous System Disorders: Oral paresthesia.

Skin and Subcutaneous Tissue Disorders: Angioedema.

Urogenital: Nephrolithiasis.

7 DRUG INTERACTIONS

See also Contraindications (4), Clinical Pharmacology (12.3).

If LEXIVA is used in combination with ritonavir, see full prescribing information for ritonavir for additional information on drug interactions.

7.1 Cytochrome P450 Inhibitors and Inducers

Amprenavir, the active metabolite of fosamprenavir, is an inhibitor of CYP3A4 metabolism and therefore should not be administered concurrently with medications with narrow therapeutic windows that are substrates of CYP3A4. Data also suggest that amprenavir induces CYP3A4.

Amprenavir is metabolized by CYP3A4. Coadministration of LEXIVA and drugs that induce CYP3A4, such as rifampin, may decrease amprenavir concentrations and reduce its therapeutic effect. Coadministration of LEXIVA and drugs that inhibit CYP3A4 may increase amprenavir concentrations and increase the incidence of adverse effects.

The potential for drug interactions with LEXIVA changes when LEXIVA is coadministered with the potent CYP3A4 inhibitor ritonavir. The magnitude of CYP3A4-mediated drug interactions (effect on amprenavir or effect on coadministered drug) may change when LEXIVA is coadministered with ritonavir. Because ritonavir is a CYP2D6 inhibitor, clinically significant interactions with drugs metabolized by CYP2D6 are possible when coadministered with LEXIVA plus ritonavir.

There are other agents that may result in serious and/or life-threatening drug interactions [see Contraindications (4)].

7.2 Drugs That Should Not Be Coadministered With LEXIVA

See Contraindications (4).

7.3 Established and Other Potentially Significant Drug Interactions

Table 7 provides a listing of established or potentially clinically significant drug interactions. Information in the table applies to LEXIVA with or without ritonavir, unless otherwise indicated.

Table 7. Established and Other Potentially Significant Drug Interactions
Concomitant Drug Class: Drug Name | Effect on Concentration of Amprenavir or Concomitant Drug | Clinical Comment
HCV/HIV-Antiviral Agents
HCV protease inhibitor:; Telaprevira | LEXIVA/ritonavir:; ↓Amprenavir; ↓Telaprevir | Coadministration of LEXIVA/ritonavir and telaprevir is not recommended.
HCV protease inhibitor:; Boceprevir | LEXIVA/ritonavir:; ↓Amprenavir (predicted); ↓Boceprevir (predicted) | Coadministration of LEXIVA/ritonavir and boceprevir is not recommended.; A pharmacokinetic interaction has been reported between boceprevir and some HIV protease inhibitors in combination with ritonavir, leading to decreased HIV protease inhibitor concentrations and, in some cases, decreased boceprevir concentrations.
Non-nucleoside reverse transcriptase inhibitor: Efavirenza | LEXIVA:; ↓Amprenavir; LEXIVA/ritonavir:; ↓Amprenavir | Appropriate doses of the combinations with respect to safety and efficacy have not been established.; An additional 100 mg/day (300 mg total) of ritonavir is recommended when efavirenz is administered with LEXIVA/ritonavir once daily. No change in the ritonavir dose is required when efavirenz is administered with LEXIVA plus ritonavir twice daily.
Non-nucleoside reverse transcriptase inhibitor:; Nevirapinea | LEXIVA:; ↓Amprenavir; ↑Nevirapine; LEXIVA/ritonavir:; ↓Amprenavir; ↑Nevirapine | Coadministration of nevirapine and LEXIVA without ritonavir is not recommended.; No dosage adjustment required when nevirapine is administered with LEXIVA/ritonavir twice daily.; The combination of nevirapine administered with LEXIVA/ritonavir once-daily regimen has not been studied.
HIV protease inhibitor:; Atazanavira | LEXIVA:; Interaction has not been evaluated.; LEXIVA/ritonavir:; ↓Atazanavir; ↔Amprenavir | Appropriate doses of the combinations with respect to safety and efficacy have not been established.
HIV protease inhibitors:; Indinavira, nelfinavira | LEXIVA:; ↑Amprenavir; Effect on indinavir and nelfinavir is not well established.; LEXIVA/ritonavir: Interaction has not been evaluated. | Appropriate doses of the combinations with respect to safety and efficacy have not been established.
HIV protease inhibitors:; Lopinavir/ritonavira | ↓Amprenavir; ↓Lopinavir | An increased rate of adverse events has been observed. Appropriate doses of the combinations with respect to safety and efficacy have not been established.
HIV protease inhibitor:; Saquinavira | LEXIVA:; ↓Amprenavir; Effect on saquinavir is not well established.; LEXIVA/ritonavir: Interaction has not been evaluated. | Appropriate doses of the combination with respect to safety and efficacy have not been established.
HIV integrase inhibitor:; Raltegravira | LEXIVA:; ↓Amprenavir; ↓Raltegravir; LEXIVA/ritonavir:; ↓Amprenavir; ↓Raltegravir | Appropriate doses of the combination with respect to safety and efficacy have not been established.
HIV CCR5 co-receptor antagonist:; Maraviroca | LEXIVA/ritonavir:; ↓Amprenavir; ↑Maraviroc | No dosage adjustment required for LEXIVA/ritonavir. The recommended dose of maraviroc is 150 mg twice daily when coadministered with LEXIVA/ritonavir. LEXIVA should be given with ritonavir when coadministered with maraviroc.
Other Agents
Antiarrhythmics:; Amiodarone, bepridil, lidocaine (systemic), and quinidine | ↑Antiarrhythmics | Use with caution. Increased exposure may be associated with life-threatening reactions such as cardiac arrhythmias. Therapeutic concentration monitoring, if available, is recommended for antiarrhythmics.
Anticoagulant:; Warfarin |  | Concentrations of warfarin may be affected. It is recommended that INR (international normalized ratio) be monitored.
Anticonvulsants:; Carbamazepine, phenobarbital, phenytoin; Phenytoina | LEXIVA:; ↓Amprenavir; LEXIVA/ritonavir:; ↑Amprenavir; ↓Phenytoin | Use with caution. LEXIVA may be less effective due to decreased amprenavir plasma concentrations in patients taking these agents concomitantly.; Plasma phenytoin concentrations should be monitored and phenytoin dose should be increased as appropriate. No change in LEXIVA/ritonavir dose is recommended.
Antidepressant:; Paroxetine, trazodone | ↓Paroxetine; ↑Trazodone | Coadministration of paroxetine with LEXIVA/ritonavir significantly decreased plasma levels of paroxetine. Any paroxetine dose adjustment should be guided by clinical effect (tolerability and efficacy).; Concomitant use of trazodone and LEXIVA with or without ritonavir may increase plasma concentrations of trazodone. Adverse events of nausea, dizziness, hypotension, and syncope have been observed following coadministration of trazodone and ritonavir. If trazodone is used with a CYP3A4 inhibitor such as LEXIVA, the combination should be used with caution and a lower dose of trazodone should be considered.
Antifungals:; Ketoconazolea, itraconazole | ↑Ketoconazole; ↑Itraconazole | Increase monitoring for adverse events.; LEXIVA:; Dose reduction of ketoconazole or itraconazole may be needed for patients receiving more than 400 mg ketoconazole or itraconazole per day.; LEXIVA/ritonavir:; High doses of ketoconazole or itraconazole (greater than 200 mg/day) are not recommended.
Anti-gout:; Colchicine | ↑Colchicine | Patients with renal or hepatic impairment should not be given colchicine with LEXIVA/ritonavir.; LEXIVA/ritonavir and coadministration of colchicine:; Treatment of gout flares:; 0.6 mg (1 tablet) x 1 dose, followed by 0.3 mg (half tablet) 1 hour later. Dose to be repeated no earlier than 3 days.; Prophylaxis of gout flares:; If the original regimen was 0.6 mg twice a day, the regimen should be adjusted to 0.3 mg once a day. If the original regimen was 0.6 mg once a day, the regimen should be adjusted to 0.3 mg once every other day.; Treatment of familial Mediterranean fever (FMF):; Maximum daily dose of 0.6 mg (may be given as 0.3 mg twice a day).; LEXIVA and coadministration of colchicine:; Treatment of gout flares:; 1.2 mg (2 tablets) x 1 dose. Dose to be repeated no earlier than 3 days.; Prophylaxis of gout flares:; If the original regimen was 0.6 mg twice a day, the regimen should be adjusted to 0.3 mg twice a day or 0.6 mg once a day. If the original regimen was 0.6 mg once a day, the regimen should be adjusted to 0.3 mg once a day.; Treatment of FMF:; Maximum daily dose of 1.2 mg (may be given as 0.6 mg twice a day).
Antimycobacterial:; Rifabutina | ↑Rifabutin and rifabutin metabolite | A complete blood count should be performed weekly and as clinically indicated to monitor for neutropenia.; LEXIVA:; A dosage reduction of rifabutin by at least half the recommended dose is required.; LEXIVA/ritonavir:; Dosage reduction of rifabutin by at least 75% of the usual dose of 300 mg/day is recommended (a maximum dose of 150 mg every other day or 3 times per week).
Benzodiazepines:; Alprazolam, clorazepate, diazepam, flurazepam | ↑Benzodiazepines | Clinical significance is unknown. A decrease in benzodiazepine dose may be needed.
Calcium channel blockers:; Diltiazem, felodipine, nifedipine, nicardipine, nimodipine, verapamil, amlodipine, nisoldipine, isradipine | ↑Calcium channel blockers | Use with caution. Clinical monitoring of patients is recommended.
Corticosteroid: Dexamethasone | ↓Amprenavir | Use with caution. LEXIVA may be less effective due to decreased amprenavir plasma concentrations.
Endothelin-receptor antagonists:; Bosentan | ↑Bosentan | Coadministration of bosentan in patients on LEXIVA:; In patients who have been receiving LEXIVA for at least 10 days, start bosentan at 62.5 mg once daily or every other day based upon individual tolerability.; Coadministration of LEXIVA in patients on bosentan:; Discontinue use of bosentan at least 36 hours prior to initiation of LEXIVA.; After at least 10 days following the initiation of LEXIVA, resume bosentan at 62.5 mg once daily or every other day based upon individual tolerability.
Histamine H2-receptor antagonists:; Cimetidine, famotidine, nizatidine, ranitidinea | LEXIVA:; ↓Amprenavir; LEXIVA/ritonavir:; Interaction not evaluated | Use with caution. LEXIVA may be less effective due to decreased amprenavir plasma concentrations.
HMG-CoA reductase inhibitors:; Atorvastatina | ↑Atorvastatin | Titrate atorvastatin dose carefully and use the lowest necessary dose; do not exceed atorvastatin 20 mg/day.
Immunosuppressants:; Cyclosporine, tacrolimus, rapamycin | ↑Immunosuppressants | Therapeutic concentration monitoring is recommended for immunosuppressant agents.
Inhaled beta-agonist:; Salmeterol | ↑Salmeterol | Concurrent administration of salmeterol with LEXIVA is not recommended. The combination may result in increased risk of cardiovascular adverse events associated with salmeterol, including QT prolongation, palpitations, and sinus tachycardia.
Inhaled/nasal steroid:; Fluticasone | LEXIVA:; ↑Fluticasone; LEXIVA/ritonavir:; ↑Fluticasone | Use with caution. Consider alternatives to fluticasone, particularly for long-term use.; May result in significantly reduced serum cortisol concentrations. Systemic corticosteroid effects including Cushing’s syndrome and adrenal suppression have been reported during postmarketing use in patients receiving ritonavir and inhaled or intranasally administered fluticasone. Coadministration of fluticasone and LEXIVA/ritonavir is not recommended unless the potential benefit to the patient outweighs the risk of systemic corticosteroid side effects.
Narcotic analgesic:; Methadone | ↓Methadone | Data suggest that the interaction is not clinically relevant; however, patients should be monitored for opiate withdrawal symptoms.
Oral contraceptives:; Ethinyl estradiol/norethindronea | LEXIVA:; ↓Amprenavir; ↓Ethinyl estradiol; LEXIVA/ritonavir:; ↓Ethinyl estradiol | Alternative methods of non-hormonal contraception are recommended.; May lead to loss of virologic response. a; Increased risk of transaminase elevations. No data are available on the use of LEXIVA/ritonavir with other hormonal therapies, such as hormone replacement therapy (HRT) for postmenopausal women.
PDE5 inhibitors:; Sildenafil, tadalafil, vardenafil | ↑Sildenafil; ↑Tadalafil; ↑Vardenafil | May result in an increase in PDE5 inhibitor-associated adverse events, including hypotension, syncope, visual disturbances, and priapism.; Use of PDE5 inhibitors for pulmonary arterial hypertension (PAH):; - Use of sildenafil (REVATIO) is contraindicated when used for the treatment of PAH [see Contraindications (4)]. - The following dose adjustments are recommended for use of tadalafil (ADCIRCA®) with LEXIVA:; Coadministration of ADCIRCA in patients on LEXIVA:; In patients receiving LEXIVA for at least one week, start ADCIRCA at 20 mg once daily. Increase to 40 mg once daily based upon individual tolerability.; Coadministration of LEXIVA in patients on ADCIRCA:; Avoid use of ADCIRCA during the initiation of LEXIVA. Stop ADCIRCA at least 24 hours prior to starting LEXIVA. After at least one week following the initiation of LEXIVA, resume ADCIRCA at 20 mg once daily. Increase to 40 mg once daily based upon individual tolerability.; Use of PDE5 inhibitors for erectile dysfunction:; LEXIVA:; Sildenafil: 25 mg every 48 hours.; Tadalafil: no more than 10 mg every 72 hours.; Vardenafil: no more than 2.5 mg every 24 hours.; LEXIVA/ritonavir:; Sildenafil: 25 mg every 48 hours.; Tadalafil: no more than 10 mg every 72 hours.; Vardenafil: no more than 2.5 mg every 72 hours.; Use with increased monitoring for adverse events.
Proton pump inhibitors:; Esomeprazolea, lansoprazole, omeprazole, pantoprazole, rabeprazole | LEXIVA:; ↔Amprenavir; ↑Esomeprazole; LEXIVA/ritonavir:; ↔Amprenavir; ↔Esomeprazole | Proton pump inhibitors can be administered at the same time as a dose of LEXIVA with no change in plasma amprenavir concentrations.
Tricyclic antidepressants:; Amitriptyline, imipramine | ↑Tricyclics | Therapeutic concentration monitoring is recommended for tricyclic antidepressants.

a See Clinical Pharmacology (12.3) Tables 10, 11, 12, or 13 for magnitude of interaction.

8 USE IN SPECIFIC POPULATIONS

8.1 Pregnancy

Pregnancy Category C. Embryo/fetal development studies were conducted in rats (dosed from day 6 to day 17 of gestation) and rabbits (dosed from day 7 to day 20 of gestation). Administration of fosamprenavir to pregnant rats and rabbits produced no major effects on embryo-fetal development; however, the incidence of abortion was increased in rabbits that were administered fosamprenavir. Systemic exposures (AUC0-24 hr) to amprenavir at these dosages were 0.8 (rabbits) to 2 (rats) times the exposures in humans following administration of the maximum recommended human dose (MRHD) of fosamprenavir alone or 0.3 (rabbits) to 0.7 (rats) times the exposures in humans following administration of the MRHD of fosamprenavir in combination with ritonavir. In contrast, administration of amprenavir was associated with abortions and an increased incidence of minor skeletal variations resulting from deficient ossification of the femur, humerus, and trochlea, in pregnant rabbits at the tested dose approximately one-twentieth the exposure seen at the recommended human dose.

The mating and fertility of the F1 generation born to female rats given fosamprenavir was not different from control animals; however, fosamprenavir did cause a reduction in both pup survival and body weights. Surviving F1 female rats showed an increased time to successful mating, an increased length of gestation, a reduced number of uterine implantation sites per litter, and reduced gestational body weights compared with control animals. Systemic exposure (AUC0-24 hr) to amprenavir in the F0 pregnant rats was approximately 2 times higher than exposures in humans following administration of the MRHD of fosamprenavir alone or approximately the same as those seen in humans following administration of the MRHD of fosamprenavir in combination with ritonavir.

There are no adequate and well-controlled studies in pregnant women. LEXIVA should be used during pregnancy only if the potential benefit justifies the potential risk to the fetus.

Antiretroviral Pregnancy Registry: To monitor maternal-fetal outcomes of pregnant women exposed to LEXIVA, an Antiretroviral Pregnancy Registry has been established. Physicians are encouraged to register patients by calling 1-800-258-4263.

8.3 Nursing Mothers

The Centers for Disease Control and Prevention recommend that HIV-infected mothers not breastfeed their infants to avoid risking postnatal transmission of HIV. Although it is not known if amprenavir is excreted in human milk, amprenavir is secreted into the milk of lactating rats. Because of both the potential for HIV transmission and the potential for serious adverse reactions in nursing infants, mothers should be instructed not to breastfeed if they are receiving LEXIVA.

8.4 Pediatric Use

The safety, pharmacokinetic profile, virologic, and immunologic responses of LEXIVA with and without ritonavir were evaluated in protease inhibitor-naive and –experienced HIV-1–infected pediatric subjects aged at least 4 weeks to less than 18 years and weighing at least 3 kg in 3 open-label trials [see Adverse Reactions (6.1), Clinical Pharmacology (12.3), Clinical Studies (14.3)]. Vomiting and neutropenia, were more frequent in pediatrics than in adults [see Adverse Reactions (6.1)]. Other adverse events occurred with similar frequency in pediatric subjects compared with adults.

Treatment with LEXIVA is not recommended in protease inhibitor-experienced pediatric patients younger than 6 months. The pharmacokinetics, safety, tolerability, and efficacy of LEXIVA in pediatric patients younger than 4 weeks have not been established [see Clinical Pharmacology (12.3)]. Available pharmacokinetic and clinical data do not support once-daily dosing of LEXIVA alone or in combination with ritonavir for any pediatrics or twice-daily dosing without ritonavir in pediatric patients younger than 2 years [see Clinical Pharmacology (12.3), Clinical Studies (14.3)]. See Dosage and Administration (2.2) for dosing recommendations for pediatric patients.

8.5 Geriatric Use

Clinical studies of LEXIVA did not include sufficient numbers of patients aged 65 and over to determine whether they respond differently from younger adults. In general, dose selection for an elderly patient should be cautious, reflecting the greater frequency of decreased hepatic, renal, or cardiac function and of concomitant disease or other drug therapy.

8.6 Hepatic Impairment

Amprenavir is principally metabolized by the liver; therefore, caution should be exercised when administering LEXIVA to patients with hepatic impairment because amprenavir concentrations may be increased [see Clinical Pharmacology (12.3)]. Patients with impaired hepatic function receiving LEXIVA with or without concurrent ritonavir require dose reduction [see Dosage and Administration (2.3)].

There are no data to support dosing recommendations for pediatric subjects with hepatic impairment.

10 OVERDOSAGE

In a healthy volunteer repeat-dose pharmacokinetic trial evaluating high-dose combinations of LEXIVA plus ritonavir, an increased frequency of Grade 2/3 ALT elevations (greater than 2.5 x ULN) was observed with LEXIVA 1,400 mg twice daily plus ritonavir 200 mg twice daily (4 of 25 subjects). Concurrent Grade 1/2 elevations in AST (greater than 1.25 x ULN) were noted in 3 of these 4 subjects. These transaminase elevations resolved following discontinuation of dosing.

There is no known antidote for LEXIVA. It is not known whether amprenavir can be removed by peritoneal dialysis or hemodialysis. If overdosage occurs, the patient should be monitored for evidence of toxicity and standard supportive treatment applied as necessary.

11 DESCRIPTION

LEXIVA (fosamprenavir calcium) is a prodrug of amprenavir, an inhibitor of HIV protease. The chemical name of fosamprenavir calcium is (3S)-tetrahydrofuran-3-yl (1S,2R)-3-[[(4-aminophenyl) sulfonyl](isobutyl)amino]-1-benzyl-2-(phosphonooxy) propylcarbamate monocalcium salt. Fosamprenavir calcium is a single stereoisomer with the (3S)(1S,2R) configuration. It has a molecular formula of C25H34CaN3O9PS and a molecular weight of 623.7. It has the following structural formula:

Fosamprenavir calcium is a white to cream-colored solid with a solubility of approximately 0.31 mg per mL in water at 25°C.

LEXIVA Tablets are available for oral administration in a strength of 700 mg of fosamprenavir as fosamprenavir calcium (equivalent to approximately 600 mg of amprenavir). Each 700 mg tablet contains the inactive ingredients colloidal silicon dioxide, croscarmellose sodium, magnesium stearate, microcrystalline cellulose, and povidone K30. The tablet film-coating contains the inactive ingredients hypromellose, iron oxide red, titanium dioxide, and triacetin.

LEXIVA Oral Suspension is available in a strength of 50 mg per mL of fosamprenavir as fosamprenavir calcium equivalent to approximately 43 mg of amprenavir. LEXIVA Oral Suspension is a white to off-white suspension with a grape-bubblegum-peppermint flavor. Each one milliliter (1 mL) contains the inactive ingredients artificial grape-bubblegum flavor, calcium chloride dihydrate, hypromellose, methylparaben, natural peppermint flavor, polysorbate 80, propylene glycol, propylparaben, purified water, and sucralose.

12 CLINICAL PHARMACOLOGY

12.1 Mechanism of Action

Fosamprenavir is an antiviral agent [see Microbiology (12.4)].

12.3 Pharmacokinetics

The pharmacokinetic properties of amprenavir after administration of LEXIVA, with or without ritonavir, have been evaluated in both healthy adult volunteers and in HIV-1-infected subjects; no substantial differences in steady-state amprenavir concentrations were observed between the 2 populations.

The pharmacokinetic parameters of amprenavir after administration of LEXIVA (with and without concomitant ritonavir) are shown in Table 8.

Table 8. Geometric Mean (95% CI) Steady-State Plasma Amprenavir Pharmacokinetic Parameters in Adults

Regimen | Cmax; (mcg/mL) | Tmax; (hours)a | AUC24; (mcg•hr/mL) | Cmin; (mcg/mL)
LEXIVA 1,400 mg b.i.d. | 4.82; (4.06-5.72) | 1.3; (0.8-4.0) | 33.0; (27.6-39.2) | 0.35; (0.27-0.46)
LEXIVA 1,400 mg q.d. plus Ritonavir 200 mg q.d. | 7.24; (6.32-8.28) | 2.1; (0.8-5.0) | 69.4; (59.7-80.8) | 1.45; (1.16-1.81)
LEXIVA 1,400 mg q.d. plus Ritonavir 100 mg q.d. | 7.93; (7.25-8.68) | 1.5; (0.75-5.0) | 66.4; (61.1-72.1) | 0.86; (0.74-1.01)
LEXIVA 700 mg b.i.d. plus Ritonavir 100 mg b.i.d. | 6.08; (5.38-6.86) | 1.5; (0.75-5.0) | 79.2; (69.0-90.6) | 2.12; (1.77-2.54)

aData shown are median (range).

The mean plasma amprenavir concentrations of the dosing regimens over the dosing intervals are displayed in Figure 1.

Figure 1. Mean (±SD) Steady-State Plasma Amprenavir Concentrations and Mean EC50 Values Against HIV from Protease Inhibitor-Naive Subjects (in the Absence of Human Serum)

Absorption and Bioavailability: After administration of a single dose of LEXIVA to HIV-1–infected subjects, the time to peak amprenavir concentration (Tmax) occurred between 1.5 and 4 hours (median 2.5 hours). The absolute oral bioavailability of amprenavir after administration of LEXIVA in humans has not been established.

After administration of a single 1,400-mg dose in the fasted state, LEXIVA Oral Suspension (50 mg per mL) and LEXIVA Tablets (700 mg) provided similar amprenavir exposures (AUC); however, the Cmax of amprenavir after administration of the suspension formulation was 14.5% higher compared with the tablet.

Effects of Food on Oral Absorption: Administration of a single 1,400-mg dose of LEXIVA Tablets in the fed state (standardized high-fat meal: 967 kcal, 67 grams fat, 33 grams protein, 58 grams carbohydrate) compared with the fasted state was associated with no significant changes in amprenavir Cmax, Tmax, or AUC0-∞ [see Dosage and Administration (2)].

Administration of a single 1,400-mg dose of LEXIVA Oral Suspension in the fed state (standardized high-fat meal: 967 kcal, 67 grams fat, 33 grams protein, 58 grams carbohydrate) compared with the fasted state was associated with a 46% reduction in Cmax, a 0.72-hour delay in Tmax, and a 28% reduction in amprenavir AUC0-∞.

Distribution: In vitro, amprenavir is approximately 90% bound to plasma proteins, primarily to alpha1-acid glycoprotein. In vitro, concentration-dependent binding was observed over the concentration range of 1 to 10 mcg per mL, with decreased binding at higher concentrations. The partitioning of amprenavir into erythrocytes is low, but increases as amprenavir concentrations increase, reflecting the higher amount of unbound drug at higher concentrations.

Metabolism: After oral administration, fosamprenavir is rapidly and almost completely hydrolyzed to amprenavir and inorganic phosphate prior to reaching the systemic circulation. This occurs in the gut epithelium during absorption. Amprenavir is metabolized in the liver by the CYP3A4 enzyme system. The 2 major metabolites result from oxidation of the tetrahydrofuran and aniline moieties. Glucuronide conjugates of oxidized metabolites have been identified as minor metabolites in urine and feces.

Amprenavir is both a substrate for and inducer of P-glycoprotein.

Elimination: Excretion of unchanged amprenavir in urine and feces is minimal. Unchanged amprenavir in urine accounts for approximately 1% of the dose; unchanged amprenavir was not detectable in feces. Approximately 14% and 75% of an administered single dose of ^14C-amprenavir can be accounted for as metabolites in urine and feces, respectively. Two metabolites accounted for greater than 90% of the radiocarbon in fecal samples. The plasma elimination half-life of amprenavir is approximately 7.7 hours.

Special Populations: Hepatic Impairment: The pharmacokinetics of amprenavir have been studied after the administration of LEXIVA in combination with ritonavir to adult HIV-1–infected subjects with mild, moderate, and severe hepatic impairment. Following 2 weeks of dosing with LEXIVA plus ritonavir, the AUC of amprenavir was increased by approximately 22% in subjects with mild hepatic impairment, by approximately 70% in subjects with moderate hepatic impairment, and by approximately 80% in subjects with severe hepatic impairment compared with HIV-1–infected subjects with normal hepatic function. Protein binding of amprenavir was decreased in subjects with hepatic impairment. The unbound fraction at 2 hours (approximate Cmax) ranged between a decrease of -7% to an increase of 57% while the unbound fraction at the end of the dosing interval (Cmin) increased from 50% to 102% [see Dosage and Administration (2.3)].

The pharmacokinetics of amprenavir have been studied after administration of amprenavir given as AGENERASE® Capsules to adult subjects with hepatic impairment. Following administration of a single 600-mg oral dose, the AUC of amprenavir was increased by approximately 2.5-fold in subjects with moderate cirrhosis and by approximately 4.5-fold in subjects with severe cirrhosis compared with healthy volunteers [see Dosage and Administration (2.3)].

Renal Impairment: The impact of renal impairment on amprenavir elimination in adults has not been studied. The renal elimination of unchanged amprenavir represents approximately 1% of the administered dose; therefore, renal impairment is not expected to significantly impact the elimination of amprenavir.

Pediatric Patients: The pharmacokinetics of amprenavir following administration of LEXIVA Oral Suspension and LEXIVA Tablets, with or without ritonavir, have been studied in a total of 212 HIV-1–infected pediatric subjects enrolled in 3 trials. LEXIVA without ritonavir was administered as 30 or 40 mg per kg twice daily to children aged 2 to 5 years. LEXIVA with ritonavir was administered as LEXIVA 30 mg per kg plus ritonavir 6 mg per kg once daily to children aged 2 to 18 years and as LEXIVA 18 to 60 mg per kg plus ritonavir 3 to 10 mg per kg twice daily to children aged at least 4 weeks to 18 years; body weights ranged from 3 to 103 kg.

Amprenavir apparent clearance decreased with increasing weight. Weight-adjusted apparent clearance was higher in children younger than 4 years, suggesting that younger children require higher mg per kg dosing of LEXIVA.

The pharmacokinetics of LEXIVA Oral Suspension in protease inhibitor-naive infants younger than 6 months (n = 9) receiving LEXIVA 45 mg per kg plus ritonavir 10 mg per kg twice daily generally demonstrated lower AUC12 and Cmin than adults receiving twice-daily LEXIVA 700 mg plus ritonavir 100 mg, the dose recommended for protease-experienced adults. The mean steady-state amprenavir AUC12, Cmax, and Cmin were 26.6 mcg•hour per mL, 6.25 mcg per mL, and 0.86 mcg per mL, respectively. These data do not support twice-daily dosing of LEXIVA alone or in combination with ritonavir in protease inhibitor-experienced patients younger than 6 months. Because of expected low amprenavir exposure and a requirement for large volume of drug, twice-daily dosing of LEXIVA alone (without ritonavir) in pediatric subjects younger than 2 years was not studied.

Pharmacokinetic parameters for LEXIVA administered with food and with ritonavir in this patient population at the recommended weight-band–based dosage regimens are provided in Table 9.

Table 9. Geometric Mean (95% CI) Steady-State Plasma Amprenavir Pharmacokinetic Parameters by Weight in Pediatric and Adolescent Subjects Aged at Least 4 Weeks to 18 Years Receiving LEXIVA With Ritonavir

Weight | Recommended Dosage Regimen | Cmax |  | AUC24 |  | Cmin
Weight | Recommended Dosage Regimen | n | (mcg/mL) | n | (mcg•hr/mL) | n | (mcg/mL)
<11 kg | LEXIVA 45 mg/kg plus; Ritonavir 7 mg/kg b.i.d | 12 | 6.00; (3.88, 9.29) | 12 | 57.3; (34.1, 96.2) | 27 | 1.65; (1.22, 2.24)
11 kg - <15 kg | LEXIVA 30 mg/kg plus; Ritonavir 3 mg/kg b.i.d | Not studieda
15 kg - <20 kg | LEXIVA 23 mg/kg plus; Ritonavir 3 mg/kg b.i.d. | 5 | 9.54; (4.63, 19.7) | 5 | 121; (54.2, 269) | 9 | 3.56; (2.33, 5.43)
>20 kg - <39 kg | LEXIVA 18 mg/kg plus; Ritonavir 3 mg/kg b.i.d. | 13 | 6.24; (5.01, 7.77) | 12 | 97.9; (77.0, 124) | 23 | 2.54; (2.11, 3.06)
≥39 kg | LEXIVA 700 mg plus; Ritonavir 100 mg b.i.d. | 15 | 5.03; (4.04, 6.26) | 15 | 72.3; (59.6, 87.6) | 42 | 1.98; (1.72, 2.29)

aRecommended dose for pediatric subjects weighing 11 kg to less than 15 kg is based on population pharmacokinetic analysis.

Subjects aged 2 to less than 6 years receiving LEXIVA 30 mg per kg twice daily without ritonavir achieved geometric mean (95% CI) amprenavir Cmax (n = 9), AUC12 (n = 9), and Cmin (n = 19) of 7.15 (5.05, 10.1), 22.3 (15.3, 32.6), and 0.513 (0.384, 0.686), respectively.

Geriatric Patients: The pharmacokinetics of amprenavir after administration of LEXIVA to patients older than 65 years have not been studied [see Use in Specific Populations (8.5)].

Gender: The pharmacokinetics of amprenavir after administration of LEXIVA do not differ between males and females.

Race: The pharmacokinetics of amprenavir after administration of LEXIVA do not differ between blacks and non-blacks.

Drug Interactions:[See Contraindications (4), Warnings and Precautions (5.1), Drug Interactions (7).]

Amprenavir, the active metabolite of fosamprenavir, is metabolized in the liver by the cytochrome P450 enzyme system. Amprenavir inhibits CYP3A4. Data also suggest that amprenavir induces CYP3A4. Caution should be used when coadministering medications that are substrates, inhibitors, or inducers of CYP3A4, or potentially toxic medications that are metabolized by CYP3A4. Amprenavir does not inhibit CYP2D6, CYP1A2, CYP2C9, CYP2C19, CYP2E1, or uridine glucuronosyltransferase (UDPGT).

Drug interaction trials were performed with LEXIVA and other drugs likely to be coadministered or drugs commonly used as probes for pharmacokinetic interactions. The effects of coadministration on AUC, Cmax, and Cmin values are summarized in Table 10 (effect of other drugs on amprenavir) and Table 12 (effect of LEXIVA on other drugs). In addition, since LEXIVA delivers comparable amprenavir plasma concentrations as AGENERASE, drug interaction data derived from trials with AGENERASE are provided in Tables 11 and 13. For information regarding clinical recommendations, [see Drug Interactions (7)].

Table 10. Drug Interactions: Pharmacokinetic Parameters for Amprenavir After Administration of LEXIVA in the Presence of the Coadministered Drug(s)

Coadministered Drug(s); and Dose(s) | Dose of LEXIVAa | n | % Change in Amprenavir Pharmacokinetic Parameters (90% CI)
Coadministered Drug(s); and Dose(s) | Dose of LEXIVAa | n | Cmax | AUC | Cmin
Antacid (MAALOX TC®); 30 mL single dose | 1,400 mg; single dose | 30 | ↓35; (↓24 to ↓42) | ↓18; (↓9 to ↓26) | ↑14; (↓7 to ↑39)
Atazanavir; 300 mg q.d. for 10 days | 700 mg b.i.d.; plus ritonavir 100 mg b.i.d.; for 10 days | 22 | ↔ | ↔ | ↔
Atorvastatin; 10 mg q.d. for 4 days | 1,400 mg b.i.d.; for 2 weeks | 16 | ↓18; (↓34 to ↑1) | ↓27; (↓41 to ↓12) | ↓12; (↓27 to ↓6)
Atorvastatin; 10 mg q.d. for 4 days | 700 mg b.i.d.; plus ritonavir 100 mg b.i.d.; for 2 weeks | 16 | ↔ | ↔ | ↔
Efavirenz; 600 mg q.d. for 2 weeks | 1,400 mg q.d.; plus ritonavir; 200 mg q.d. for; 2 weeks | 16 | ↔ | ↓13; (↓30 to ↑7) | ↓36; (↓8 to ↓56)
Efavirenz; 600 mg q.d. plus additional; ritonavir 100 mg q.d. for; 2 weeks | 1,400 mg q.d.; plus ritonavir; 200 mg q.d. for; 2 weeks | 16 | ↑18; (↑1 to ↑38) | ↑11; (0 to ↑24) | ↔
Efavirenz; 600 mg q.d. for 2 weeks | 700 mg b.i.d.; plus ritonavir; 100 mg b.i.d. for; 2 weeks | 16 | ↔ | ↔ | ↓17; (↓4 to ↓29)
Esomeprazole; 20 mg q.d. for 2 weeks | 1,400 mg b.i.d. for 2 weeks | 25 | ↔ | ↔ | ↔
Esomeprazole; 20 mg q.d. for 2 weeks | 700 mg b.i.d.; plus ritonavir; 100 mg b.i.d. for; 2 weeks | 23 | ↔ | ↔ | ↔
Ethinyl estradiol/ norethindrone; 0.035 mg/0.5 mg q.d. for 21 days | 700 mg b.i.d.; plus ritonavirb; 100 mg b.i.d.; for 21 days | 25 | ↔c | ↔c | ↔c
Ketoconazoled; 200 mg q.d. for 4 days | 700 mg b.i.d.; plus ritonavir; 100 mg b.i.d. for; 4 days | 15 | ↔ | ↔ | ↔
Lopinavir/ritonavir; 533 mg/133 mg b.i.d. | 1,400 mg b.i.d.; for 2 weeks | 18 | ↓13e | ↓26e | ↓42e
Lopinavir/ritonavir; 400 mg/100 mg b.i.d. for; 2 weeks | 700 mg b.i.d.; plus ritonavir; 100 mg b.i.d. for 2 weeks | 18 | ↓58; (↓42 to ↓70) | ↓63; (↓51 to ↓72) | ↓65; (↓54 to ↓73)
Maraviroc; 300 mg b.i.d. for 10 days | 700 mg b.i.d.; plus ritonavir; 100 mg b.i.d. for; 20 days | 14 | ↓34; (↓25 to ↓41) | ↓35; (↓29 to ↓41) | ↓36; (↓27 to ↓43)
Maraviroc; 300 mg q.d. for 10 days | 1,400 mg q.d.; plus ritonavir; 100 mg q.d. for 20 days | 14 | ↓29; (↓20 to ↓38) | ↓30; (↓23 to ↓36) | ↓15; (↓3 to ↓25)
Methadone; 70 to 120 mg q.d. for 2 weeks | 700 mg b.i.d.; plus ritonavir; 100 mg b.i.d. for 2 weeks | 19 | ↔c | ↔c | ↔c
Nevirapine; 200 mg b.i.d. for 2 weeksf | 1,400 mg b.i.d. for 2 weeks | 17 | ↓25; (↓37 to ↓10) | ↓33; (↓45 to ↓20) | ↓35; (↓50 to ↓15)
Nevirapine; 200 mg b.i.d. for 2 weeksf | 700 mg b.i.d.; plus ritonavir 100 mg b.i.d. for 2 weeks | 17 | ↔ | ↓11; (↓23 to ↑3) | ↓19; (↓32 to ↓4)
Phenytoin; 300 mg q.d. for 10 days | 700 mg b.i.d.; plus ritonavir 100 mg b.i.d. for 10 days | 13 | ↔ | ↑20; (↑8 to ↑34) | ↑19; (↑6 to ↑33)
Raltegravir; 400 mg b.i.d. for 14 days | 1,400 mg b.i.d. for 14 days (fasted) | 14 | ↓27; (↓46 to ↔) | ↓36; (↓53 to ↓13) | ↓43g; (↓59 to ↓21)
Raltegravir; 400 mg b.i.d. for 14 days | 1,400 mg b.i.d. for 14 daysh | 14 | ↓15; (↓27 to ↓1) | ↓17; (↓27 to ↓6) | ↓32g; (↓53 to ↓1)
Raltegravir; 400 mg b.i.d. for 14 days | 700 mg b.i.d.; plus ritonavir 100 mg b.i.d. for 14 days (fasted) | 14 | ↓14; (↓39 to ↑20) | ↓17; (↓38 to ↑12) | ↓20g; (↓45 to ↑17)
Raltegravir; 400 mg b.i.d. for 14 days | 700 mg b.i.d.; plus ritonavir 100 mg b.i.d. for 14 daysh | 12 | ↓25; (↓42 to ↓2) | ↓25; (↓44 to ↔) | ↓33g; (↓52 to ↓7)
Raltegravir; 400 mg b.i.d. for 14 days | 1,400 mg q.d.; plus ritonavir; 100 mg q.d. for 14 days (fasted) | 13 | ↓18; (↓34 to ↔) | ↓24; (↓41 to ↔) | ↓50g; (↓64 to ↓31)
Raltegravir; 400 mg b.i.d. for 14 days | 1,400 mg q.d.; plus ritonavir; 100 mg q.d. for 14 daysh | 14 | ↑27; (↓1 to ↑62) | ↑13; (↓7 to ↑38) | 17g; (↓45 to ↑26)
Ranitidine; 300 mg single dose; (administered 1 hour before fosamprenavir) | 1,400 mg; single dose | 30 | ↓51; (↓43 to ↓58) | ↓30; (↓22 to ↓37) | ↔ (↓19 to ↑21)
Rifabutin; 150 mg q.o.d. for 2 weeks | 700 mg b.i.d.; plus ritonavir 100 mg b.i.d. for 2 weeks | 15 | ↑36c; (↑18 to ↑55) | ↑35c; (↑17 to ↑56) | ↑17c; (↓1 to ↑39)
Telaprevir; 750 mg q. 8 hr for 10 days | 700 mg b.i.d.; plus ritonavir 100 mg b.i.d. for 20 days | 18 | ↓35; (↓30 to ↓41) | ↓47; (↓42 to ↓51) | ↓56; (↓50 to ↓60)
Telaprevir; 1,125 mg q. 12 hr for 4 days | 700 mg b.i.d.; plus ritonavir 100 mg b.i.d. for 24 days | 17 | ↓40i; (↓33 to ↓45) | ↓49i; (↓45 to ↓53) | ↓58i; (↓53 to ↓63)
Tenofovir; 300 mg q.d. for 4 to 48 weeks | 700 mg b.i.d.; plus ritonavir 100 mg b.i.d. for; 4 to 48 weeks | 45 | NA | NA | ↔j
Tenofovir; 300 mg q.d. for 4 to 48 weeks | 1,400 mg q.d.; plus ritonavir; 200 mg q.d. for; 4 to 48 weeks | 60 | NA | NA | ↔j

aConcomitant medication is also shown in this column where appropriate.

bRitonavir Cmax, AUC, and Cmin increased by 63%, 45%, and 13%, respectively, compared with historical control.

cCompared with historical control.

dSubjects were receiving LEXIVA/ritonavir for 10 days prior to the 4-day treatment period with both ketoconazole and LEXIVA/ritonavir.

eCompared with LEXIVA 700 mg/ritonavir 100 mg b.i.d. for 2 weeks.

fSubjects were receiving nevirapine for at least 12 weeks prior to trial.

gClast (C12 hr or C24 hr).

hDoses of LEXIVA and raltegravir were given with food on pharmacokinetic sampling days and without regard to food all other days.

iN = 18 for Cmin.

jCompared with parallel control group.

↑ = Increase; ↓= Decrease; ↔ = No change (↑or ↓ less than or equal to 10%), NA = Not applicable.

Table 11. Drug Interactions: Pharmacokinetic Parameters for Amprenavir After Administration of AGENERASE in the Presence of the Coadministered Drug(s)

Coadministered Drug(s); and Dose(s) | Dose of AGENERASEa | n | % Change in Amprenavir Pharmacokinetic Parameters; (90% CI)
Coadministered Drug(s); and Dose(s) | Dose of AGENERASEa | n | Cmax | AUC | Cmin
Abacavir; 300 mg b.i.d. for 2 to 3 weeks | 900 mg b.i.d.; for 2 to 3 weeks | 4 | ↔a | ↔a | ↔a
Clarithromycin; 500 mg b.i.d. for 4 days | 1,200 mg b.i.d.; for 4 days | 12 | ↑15; (↑1 to ↑31) | ↑18; (↑8 to ↑29) | ↑39; (↑31 to ↑47)
Delavirdine; 600 mg b.i.d. for 10 days | 600 mg b.i.d.; for 10 days | 9 | ↑40b | ↑130b | ↑125b
Ethinyl estradiol/norethindrone; 0.035 mg/1 mg for 1 cycle | 1,200 mg b.i.d.; for 28 days | 10 | ↔ | ↓22; (↓35 to ↓8) | ↓20; (↓41 to ↑8)
Indinavir; 800 mg t.i.d. for 2 weeks; (fasted) | 750 or 800 mg t.i.d. for 2 weeks (fasted) | 9 | ↑18; (↑13 to ↑58) | ↑33; (↑2 to ↑73) | ↑25; (↓27 to ↑116)
Ketoconazole; 400 mg single dose | 1,200 mg; single dose | 12 | ↓16; (↓25 to ↓6) | ↑31; (↑20 to ↑42) | NA
Lamivudine; 150 mg single dose | 600 mg; single dose | 11 | ↔ | ↔ | NA
Methadone; 44 to 100 mg q.d. for; >30 days | 1,200 mg b.i.d.; for 10 days | 16 | ↓27c | ↓30c | ↓25c
Nelfinavir; 750 mg t.i.d. for 2 weeks; (fed) | 750 or 800 mg t.i.d. for 2 weeks (fed) | 6 | ↓14; (↓38 to ↑20) | ↔ | ↑189; (↑52 to ↑448)
Rifabutin; 300 mg q.d. for 10 days | 1,200 mg b.i.d.; for 10 days | 5 | ↔ | ↓15; (↓28 to 0) | ↓15; (↓38 to ↑17)
Rifampin; 300 mg q.d. for 4 days | 1,200 mg b.i.d.; for 4 days | 11 | ↓70; (↓76 to ↓62) | ↓82; (↓84 to ↓78) | ↓92; (↓95 to ↓89)
Saquinavir; 800 mg t.i.d. for 2 weeks; (fed) | 750 or 800 mg t.i.d. for 2 weeks (fed) | 7 | ↓37; (↓54 to ↓14) | ↓32; (↓49 to ↓9) | ↓14; (↓52 to ↑54)
Zidovudine; 300 mg single dose | 600 mg; single dose | 12 | ↔ | ↑13; (↓2 to ↑31) | NA

aCompared with parallel control group.

bMedian percent change; confidence interval not reported.

cCompared with historical data.

↑ = Increase; ↓ = Decrease; ↔ = No change (↑or ↓ less than 10%); NA = Cmin not calculated for single‑dose trial.

Table 12. Drug Interactions: Pharmacokinetic Parameters for Coadministered Drug in the Presence of Amprenavir After Administration of LEXIVA
Coadministered Drug(s); and Dose(s) | Dose of LEXIVAa | n | % Change in Pharmacokinetic Parameters of Coadministered Drug (90% CI)
Coadministered Drug(s); and Dose(s) | Dose of LEXIVAa | n | Cmax | AUC | Cmin
Atazanavir; 300 mg q.d. for 10 daysb | 700 mg b.i.d.; plus ritonavir 100 mg b.i.d.; for 10 days | 21 | ↓24; (↓39 to ↓6) | ↓22; (↓34 to ↓9) | ↔
Atorvastatin; 10 mg q.d. for 4 days | 1,400 mg b.i.d.; for 2 weeks | 16 | ↑304; (↑205 to ↑437) | ↑130; (↑100 to ↑164) | ↓10; (↓27 to ↑12)
Atorvastatin; 10 mg q.d. for 4 days | 700 mg b.i.d.; plus ritonavir 100 mg b.i.d.; for 2 weeks | 16 | ↑184; (↑126 to ↑257) | ↑153; (↑115 to ↑199) | ↑73; (↑45 to ↑108)
Esomeprazole; 20 mg q.d. for 2 weeks | 1,400 mg b.i.d. for 2 weeks | 25 | ↔ | ↑55; (↑39 to ↑73) | ND
Esomeprazole; 20 mg q.d. for 2 weeks | 700 mg b.i.d.; plus ritonavir; 100 mg b.i.d. for 2 weeks | 23 | ↔ | ↔ | ND
Ethinyl estradiolc; 0.035 mg q.d. for 21 days | 700 mg b.i.d.; plus ritonavir; 100 mg b.i.d.; for 21 days | 25 | ↓28; (↓21 to ↓35) | ↓37; (↓30 to ↓42) | ND
Ketoconazoled; 200 mg q.d. for 4 days | 700 mg b.i.d.; plus ritonavir; 100 mg b.i.d. for 4 days | 15 | ↑25; (↑0 to ↑56) | ↑169; (↑108 to ↑248) | ND
Lopinavir/ritonavire; 533 mg/133 mg b.i.d. for; 2 weeks | 1,400 mg b.i.d.; for 2 weeks | 18 | ↔f | ↔f | ↔f
Lopinavir/ritonavire; 400 mg/100 mg b.i.d. for; 2 weeks | 700 mg b.i.d.; plus ritonavir 100 mg b.i.d. for 2 weeks | 18 | ↑30; (↓15 to ↑47) | ↑37; (↓20 to ↑55) | ↑52; (↓28 to ↑82)
Maraviroc; 300 mg b.i.d. for 10 days | 700 mg b.i.d.; plus ritonavir; 100 mg b.i.d. for; 20 days | 14 | ↑52; (↑27 to ↑82) | ↑149; (↑119 to ↑182) | ↑374; (↑303 to ↑457)
Maraviroc; 300 mg q.d. for 10 days | 1,400 mg q.d.; plus ritonavir; 100 mg q.d. for 20 days | 14 | ↑45; (↑20 to ↑74) | ↑126; (↑99 to ↑158) | ↑80; (↑53 to ↑113)
Methadone; 70 to 120 mg q.d. for; 2 weeks | 700 mg b.i.d.; plus ritonavir 100 mg b.i.d. for 2 weeks | 19 | R-Methadone (active)
Methadone; 70 to 120 mg q.d. for; 2 weeks | 700 mg b.i.d.; plus ritonavir 100 mg b.i.d. for 2 weeks |  | ↓21g; (↓30 to ↓12) | ↓18g; (↓27 to ↓8) | ↓11g; (↓21 to ↑1)
Methadone; 70 to 120 mg q.d. for; 2 weeks | 700 mg b.i.d.; plus ritonavir 100 mg b.i.d. for 2 weeks |  | S-Methadone (inactive)
Methadone; 70 to 120 mg q.d. for; 2 weeks | 700 mg b.i.d.; plus ritonavir 100 mg b.i.d. for 2 weeks |  | ↓43g; (↓49 to ↓37) | ↓43g; (↓50 to ↓36) | ↓41g; (↓49 to ↓31)
Nevirapine; 200 mg b.i.d. for 2 weeksh | 1,400 mg b.i.d.; for 2 weeks | 17 | ↑25; (↑14 to ↑37) | ↑29; (↑19 to ↑40) | ↑34; (↑20 to ↑49)
Nevirapine; 200 mg b.i.d. for 2 weeksh | 700 mg b.i.d. plus ritonavir 100 mg b.i.d. for 2 weeks | 17 | ↑13; (↑3 to ↑24) | ↑14; (↑5 to ↑24) | ↑22; (↑9 to ↑35)
Norethindronec; 0.5 mg q.d. for 21 days | 700 mg b.i.d.; plus ritonavir; 100 mg b.i.d.; for 21 days | 25 | ↓38; (↓32 to ↓44) | ↓34; (↓30 to ↓37) | ↓26; (↓20 to ↓32)
Phenytoin; 300 mg q.d. for 10 days | 700 mg b.i.d.; plus ritonavir 100 mg b.i.d. for 10 days | 14 | ↓20; (↓12 to ↓27) | ↓22; (↓17 to ↓27) | ↓29; (↓23 to ↓34)
Rifabutin; 150 mg every other day for 2 weeks i | 700 mg b.i.d.; plus ritonavir 100 mg b.i.d. for 2 weeks | 15 | ↓14; (↓28 to ↑4) | ↔ | ↑28; (↑12 to ↑46)
(25-O-desacetylrifabutin; metabolite) |  |  | ↑579; (↑479 to ↑698) | ↑1,120; (↑965 to ↑1,300) | ↑2,510; (↑1,910 to ↑3,300)
Rifabutin + 25-O-; desacetylrifabutin; metabolite |  |  | NA | ↑64; (↑46 to ↑84) | NA
Rosuvastatin; 10 mg single dose | 700 mg b.i.d.; plus ritonavir 100 mg b.i.d. for 7 days |  | ↑45 | ↑8 | NA
Telaprevir; 750 mg q. 8 hr for 10 days | 700 mg b.i.d.; plus ritonavir 100 mg b.i.d. for 20 days | 18 | ↓33; (↓29 to ↓37) | ↓32; (↓28 to ↓37) | ↓30; (↓23 to ↓36)

aConcomitant medication is also shown in this column where appropriate.

bComparison arm of atazanavir 300 mg q.d. plus ritonavir 100 mg q.d. for 10 days.

cAdministered as a combination oral contraceptive tablet: ethinyl estradiol 0.035 mg/norethindrone 0.5 mg.

dSubjects were receiving LEXIVA/ritonavir for 10 days prior to the 4-day treatment period with both ketoconazole and LEXIVA/ritonavir.

eData represent lopinavir concentrations.

fCompared with lopinavir 400 mg/ritonavir 100 mg b.i.d. for 2 weeks.

gDose normalized to methadone 100 mg. The unbound concentration of the active moiety, R‑methadone, was unchanged.

hSubjects were receiving nevirapine for at least 12 weeks prior to trial.

iComparison arm of rifabutin 300 mg q.d. for 2 weeks. AUC is AUC(0-48 hr).

↑ = Increase; ↓= Decrease; ↔ = No change (↑or ↓less than 10%); ND = Interaction cannot be determined as Cmin was below the lower limit of quantitation.

Table 13. Drug Interactions: Pharmacokinetic Parameters for Coadministered Drug in the Presence of Amprenavir After Administration of AGENERASE
Coadministered Drug(s) and Dose(s) | Dose of AGENERASE |  | % Change in Pharmacokinetic Parameters of Coadministered Drug (90% CI)
Coadministered Drug(s) and Dose(s) | Dose of AGENERASE | n | Cmax | AUC | Cmin
Abacavir; 300 mg b.i.d. for 2 to 3 weeks | 900 mg b.i.d; for 2 to 3 weeks | 4 | ↔a | ↔a | ↔a
Clarithromycin; 500 mg b.i.d. for 4 days | 1,200 mg b.i.d.; for 4 days | 12 | ↓10; (↓24 to ↑7) | ↔ | ↔
Delavirdine; 600 mg b.i.d. for 10 days | 600 mg b.i.d.; for 10 days | 9 | ↓47b | ↓61b | ↓88b
Ethinyl estradiol; 0.035 mg for 1 cycle | 1,200 mg b.i.d.; for 28 days | 10 | ↔ | ↔ | ↑32; (↓3 to ↑79)
Indinavir; 800 mg t.i.d. for 2 weeks (fasted) | 750 mg or 800 mg t.i.d. for 2 weeks (fasted) | 9 | ↓22a | ↓38a | ↓27a
Ketoconazole; 400 mg single dose | 1,200 mg; single dose | 12 | ↑19; (↑8 to ↑33) | ↑44; (↑31 to ↑59) | NA
Lamivudine; 150 mg single dose | 600 mg; single dose | 11 | ↔ | ↔ | NA
Methadone; 44 to 100 mg q.d. for; >30 days | 1,200 mg b.i.d.; for 10 days | 16 | R-Methadone (active)
Methadone; 44 to 100 mg q.d. for; >30 days | 1,200 mg b.i.d.; for 10 days | 16 | ↓25; (↓32 to ↓18) | ↓13; (↓21 to ↓5) | ↓21; (↓32 to ↓9)
Methadone; 44 to 100 mg q.d. for; >30 days | 1,200 mg b.i.d.; for 10 days | 16 | S-Methadone (inactive)
Methadone; 44 to 100 mg q.d. for; >30 days | 1,200 mg b.i.d.; for 10 days | 16 | ↓48; (↓55 to ↓40) | ↓40; (↓46 to ↓32) | ↓53; (↓60 to ↓43)
Nelfinavir; 750 mg t.i.d. for 2 weeks (fed) | 750 mg or 800 mg t.i.d. for 2 weeks (fed) | 6 | ↑12a | ↑15a | ↑14a
Norethindrone; 1 mg for 1 cycle | 1,200 mg b.i.d.; for 28 days | 10 | ↔ | ↑18; (↑1 to ↑38) | ↑45; (↑13 to ↑88)
Rifabutin; 300 mg q.d. for 10 days | 1,200 mg b.i.d.; for 10 days | 5 | ↑119; (↑82 to ↑164) | ↑193; (↑156 to ↑235) | ↑271; (↑171 to ↑409)
Rifampin; 300 mg q.d. for 4 days | 1,200 mg b.i.d.; for 4 days | 11 | ↔ | ↔ | ND
Saquinavir; 800 mg t.i.d. for 2 weeks (fed) | 750 mg or 800 mg t.i.d. for 2 weeks (fed) | 7 | ↑21a | ↓19a | ↓48a
Zidovudine; 300 mg single dose | 600 mg; single dose | 12 | ↑40; (↑14 to ↑71) | ↑31; (↑19 to ↑45) | NA

aCompared with historical data.

bMedian percent change; confidence interval not reported.

↑ = Increase; ↓ = Decrease; ↔= No change (↑or ↓ less than 10%); NA = Cmin not calculated for single-dose trial; ND = Interaction cannot be determined as Cmin was below the lower limit of quantitation.

12.4 Microbiology

Mechanism of Action: Fosamprenavir is a prodrug that is rapidly hydrolyzed to amprenavir by cellular phosphatases in the gut epithelium as it is absorbed. Amprenavir is an inhibitor of HIV-1 protease. Amprenavir binds to the active site of HIV-1 protease and thereby prevents the processing of viral Gag and Gag-Pol polyprotein precursors, resulting in the formation of immature non-infectious viral particles.

Antiviral Activity: Fosamprenavir has little or no antiviral activity in cell culture. The antiviral activity of amprenavir was evaluated against HIV-1 IIIB in both acutely and chronically infected lymphoblastic cell lines (MT-4, CEM-CCRF, H9) and in peripheral blood lymphocytes in cell culture. The 50% effective concentration (EC50) of amprenavir ranged from 0.012 to 0.08 microM in acutely infected cells and was 0.41 microM in chronically infected cells (1 microM = 0.50 mcg per mL). The median EC50 value of amprenavir against HIV-1 isolates from clades A to G was 0.00095 microM in peripheral blood mononuclear cells (PBMCs). Similarly, the EC50 values for amprenavir against monocytes/macrophage tropic HIV-1 isolates (clade B) ranged from 0.003 to 0.075 microM in monocyte/macrophage cultures. The EC50 values of amprenavir against HIV-2 isolates grown in PBMCs were higher than those for HIV-1 isolates, and ranged from 0.003 to 0.11 microM. Amprenavir exhibited synergistic anti–HIV–1 activity in combination with the nucleoside reverse transcriptase inhibitors (NRTIs) abacavir, didanosine, lamivudine, stavudine, tenofovir, and zidovudine; the non-nucleoside reverse transcriptase inhibitors (NNRTIs) delavirdine and efavirenz; and the protease inhibitors atazanavir and saquinavir. Amprenavir exhibited additive anti–HIV–1 activity in combination with the NNRTI nevirapine, the protease inhibitors indinavir, lopinavir, nelfinavir, and ritonavir; and the fusion inhibitor enfuvirtide. These drug combinations have not been adequately studied in humans.

Resistance: HIV-1 isolates with decreased susceptibility to amprenavir have been selected in cell culture and obtained from subjects treated with fosamprenavir. Genotypic analysis of isolates from treatment-naive subjects failing amprenavir-containing regimens showed substitutions in the HIV-1 protease gene resulting in amino acid substitutions primarily at positions V32I, M46I/L, I47V, I50V, I54L/M, and I84V, as well as substitutions in the p7/p1 and p1/p6 Gag and Gag-Pol polyprotein precursor cleavage sites. Some of these amprenavir resistance-associated substitutions have also been detected in HIV-1 isolates from antiretroviral-naive subjects treated with LEXIVA. Of the 488 antiretroviral-naive subjects treated with LEXIVA 1,400 mg twice daily or LEXIVA 1,400 mg plus ritonavir 200 mg once daily in Trials APV30001 and APV30002, respectively, 61 subjects (29 receiving LEXIVA and 32 receiving LEXIVA/ritonavir) with virologic failure (plasma HIV-1 RNA greater than 1,000 copies per mL on 2 occasions on or after Week 12) were genotyped. Five of the 29 antiretroviral-naive subjects (17%) receiving LEXIVA without ritonavir in Trial APV30001 had evidence of genotypic resistance to amprenavir: I54L/M (n = 2), I54L + L33F (n = 1), V32I + I47V (n = 1), and M46I + I47V (n = 1). No amprenavir resistance-associated substitutions were detected in antiretroviral-naive subjects treated with LEXIVA/ritonavir for 48 weeks in Trial APV30002. However, the M46I and I50V substitutions were detected in isolates from 1 virologic failure subject receiving LEXIVA/ritonavir once daily at Week 160 (HIV-1 RNA greater than 500 copies per mL). Upon retrospective analysis of stored samples using an ultrasensitive assay, these resistant substitutions were traced back to Week 84 (76 weeks prior to clinical virologic failure).

Cross-Resistance: Varying degrees of cross-resistance among HIV-1 protease inhibitors have been observed. An association between virologic response at 48 weeks (HIV-1 RNA level less than 400 copies per mL) and protease inhibitor-resistance substitutions detected in baseline HIV-1 isolates from protease inhibitor-experienced subjects receiving LEXIVA/ritonavir twice daily (n = 88), or lopinavir/ritonavir twice daily (n = 85) in Trial APV30003 is shown in Table 14. The majority of subjects had previously received either one (47%) or 2 protease inhibitors (36%), most commonly nelfinavir (57%) and indinavir (53%). Out of 102 subjects with baseline phenotypes receiving twice-daily LEXIVA/ritonavir, 54% (n = 55) had resistance to at least one protease inhibitor, with 98% (n = 54) of those having resistance to nelfinavir. Out of 97 subjects with baseline phenotypes in the lopinavir/ritonavir arm, 60% (n = 58) had resistance to at least one protease inhibitor, with 97% (n = 56) of those having resistance to nelfinavir.

Table 14. Responders at Trial Week 48 by Presence of Baseline Protease Inhibitor Resistance-Associated Substitutionsa
Protease Inhibitor Resistance-Associated Substitutionsb | LEXIVA/Ritonavir b.i.d.; (n = 88) |  | Lopinavir/Ritonavir b.i.d.; (n = 85)
D30N | 21/22 | 95% | 17/19 | 89%
N88D/S | 20/22 | 91% | 12/12 | 100%
L90M | 16/31 | 52% | 17/29 | 59%
M46I/L | 11/22 | 50% | 12/24 | 50%
V82A/F/T/S | 2/9 | 22% | 6/17 | 35%
I54V | 2/11 | 18% | 6/11 | 55%
I84V | 1/6 | 17% | 2/5 | 40%

aResults should be interpreted with caution because the subgroups were small.

bMost subjects had greater than 1 protease inhibitor resistance-associated substitution at baseline.

The virologic response based upon baseline phenotype was assessed. Baseline isolates from protease inhibitor-experienced subjects responding to LEXIVA/ritonavir twice daily had a median shift in susceptibility to amprenavir relative to a standard wild-type reference strain of 0.7 (range: 0.1 to 5.4, n = 62), and baseline isolates from individuals failing therapy had a median shift in susceptibility of 1.9 (range: 0.2 to 14, n = 29). Because this was a select patient population, these data do not constitute definitive clinical susceptibility break points. Additional data are needed to determine clinically relevant break points for LEXIVA.

Isolates from 15 of the 20 subjects receiving twice-daily LEXIVA/ritonavir up to Week 48 and experiencing virologic failure/ongoing replication were subjected to genotypic analysis. The following amprenavir resistance-associated substitutions were found either alone or in combination: V32I, M46I/L, I47V, I50V, I54L/M, and I84V. Isolates from 4 of the 16 subjects continuing to receive twice-daily LEXIVA/ritonavir up to Week 96 who experienced virologic failure underwent genotypic analysis. Isolates from 2 subjects contained amprenavir resistance-associated substitutions: V32I, M46I, and I47V in 1 isolate and I84V in the other.

13 NONCLINICAL TOXICOLOGY

13.1 Carcinogenesis, Mutagenesis, Impairment of Fertility

In long-term carcinogenicity studies, fosamprenavir was administered orally for up to 104 weeks at doses of 250, 400, or 600 mg per kg per day in mice and at doses of 300, 825, or 2,250 mg per kg per day in rats. Exposures at these doses were 0.3- to 0.7-fold (mice) and 0.7- to 1.4-fold (rats) those in humans given 1,400 mg twice daily of fosamprenavir alone, and 0.2- to 0.3-fold (mice) and 0.3- to 0.7-fold (rats) those in humans given 1,400 mg once daily of fosamprenavir plus 200 mg ritonavir once daily. Exposures in the carcinogenicity studies were 0.1- to 0.3-fold (mice) and 0.3- to 0.6-fold (rats) those in humans given 700 mg of fosamprenavir plus 100 mg ritonavir twice daily. There was an increase in hepatocellular adenomas and hepatocellular carcinomas at all doses in male mice and at 600 mg per kg per day in female mice, and in hepatocellular adenomas and thyroid follicular cell adenomas at all doses in male rats, and at 835 mg per kg per day and 2,250 mg per kg per day in female rats. The relevance of the hepatocellular findings in the rodents for humans is uncertain. Repeat dose studies with fosamprenavir in rats produced effects consistent with enzyme induction, which predisposes rats, but not humans, to thyroid neoplasms. In addition, in rats only there was an increase in interstitial cell hyperplasia at 825 mg per kg per day and 2,250 mg per kg per day, and an increase in uterine endometrial adenocarcinoma at 2,250 mg per kg per day. The incidence of endometrial findings was slightly increased over concurrent controls, but was within background range for female rats. The relevance of the uterine endometrial adenocarcinoma findings in rats for humans is uncertain.

Fosamprenavir was not mutagenic or genotoxic in a battery of in vitro and in vivo assays. These assays included bacterial reverse mutation (Ames), mouse lymphoma, rat micronucleus, and chromosome aberrations in human lymphocytes.

The effects of fosamprenavir on fertility and general reproductive performance were investigated in male (treated for 4 weeks before mating) and female rats (treated for 2 weeks before mating through postpartum day 6). Systemic exposures (AUC0-24 hr) to amprenavir in these studies were 3 (males) to 4 (females) times higher than exposures in humans following administration of the MRHD of fosamprenavir alone or similar to those seen in humans following administration of fosamprenavir in combination with ritonavir. Fosamprenavir did not impair mating or fertility of male or female rats and did not affect the development and maturation of sperm from treated rats.

14 CLINICAL STUDIES

14.1 Therapy-Naive Adult Trials

APV30001: A randomized, open-label trial evaluated treatment with LEXIVA Tablets (1,400 mg twice daily) versus nelfinavir (1,250 mg twice daily) in 249 antiretroviral treatment-naive subjects. Both groups of subjects also received abacavir (300 mg twice daily) and lamivudine (150 mg twice daily).

The mean age of the subjects in this trial was 37 years (range: 17 to 70 years); 69% of the subjects were male, 20% were CDC Class C (AIDS), 24% were Caucasian, 32% were black, and 44% were Hispanic. At baseline, the median CD4+ cell count was 212 cells per mm^3 (range: 2 to 1,136 cells per mm^3; 18% of subjects had a CD4+ cell count of less than 50 cells per mm^3 and 30% were in the range of 50 to less than 200 cells per mm^3). Baseline median HIV-1 RNA was 4.83 log10 copies per mL (range: 1.69 to 7.41 log10 copies per mL; 45% of subjects had greater than 100,000 copies per mL).

The outcomes of randomized treatment are provided in Table 15.

Table 15. Outcomes of Randomized Treatment Through Week 48 (APV30001)
Outcome; (Rebound or discontinuation = failure) | LEXIVA; 1,400 mg b.i.d.; (n = 166) | Nelfinavir; 1,250 mg b.i.d.; (n = 83)
Respondera | 66% (57%) | 52% (42%)
Virologic failure | 19% | 32%
Rebound | 16% | 19%
Never suppressed through Week 48 | 3% | 13%
Clinical progression | 1% | 1%
Death | 0% | 1%
Discontinued due to adverse reactions | 4% | 2%
Discontinued due to other reasonsb | 10% | 10%

aSubjects achieved and maintained confirmed HIV-1 RNA less than 400 copies per mL (less than 50 copies per mL) through Week 48 (Roche AMPLICOR HIV-1 MONITOR Assay Version 1.5).

bIncludes consent withdrawn, lost to follow up, protocol violations, those with missing data, and other reasons.

Treatment response by viral load strata is shown in Table 16.

Table 16. Proportions of Responders Through Week 48 by Screening Viral Load (APV30001)
Screening Viral Load HIV-1 RNA (copies/mL) | LEXIVA; 1,400 mg b.i.d. |  | Nelfinavir; 1,250 mg b.i.d.
Screening Viral Load HIV-1 RNA (copies/mL) | <400 copies/mL | n | <400 copies/mL | n
≤100,000 | 65% | 93 | 65% | 46
>100,000 | 67% | 73 | 36% | 37

Through 48 weeks of therapy, the median increases from baseline in CD4+ cell counts were 201 cells per mm^3 in the group receiving LEXIVA and 216 cells per mm^3 in the nelfinavir group.

APV30002: A randomized, open-label trial evaluated treatment with LEXIVA Tablets (1,400 mg once daily) plus ritonavir (200 mg once daily) versus nelfinavir (1,250 mg twice daily) in 649 treatment-naive subjects. Both treatment groups also received abacavir (300 mg twice daily) and lamivudine (150 mg twice daily).

The mean age of the subjects in this trial was 37 years (range: 18 to 69 years); 73% of the subjects were male, 22% were CDC Class C, 53% were Caucasian, 36% were black, and 8% were Hispanic. At baseline, the median CD4+ cell count was 170 cells per mm^3 (range: 1 to 1,055 cells per mm^3; 20% of subjects had a CD4+ cell count of less than 50 cells per mm^3 and 35% were in the range of 50 to less than 200 cells per mm^3). Baseline median HIV-1 RNA was 4.81 log10 copies per mL (range: 2.65 to 7.29 log10 copies per mL; 43% of subjects had greater than 100,000 copies per mL).

The outcomes of randomized treatment are provided in Table 17.

Table 17. Outcomes of Randomized Treatment Through Week 48 (APV30002)

Outcome; (Rebound or discontinuation = failure) | LEXIVA 1,400 mg q.d./; Ritonavir 200 mg q.d.; (n = 322) | Nelfinavir; 1,250 mg b.i.d.; (n = 327)
Respondera | 69% (58%) | 68% (55%)
Virologic failure | 6% | 16%
Rebound | 5% | 8%
Never suppressed through Week 48 | 1% | 8%
Death | 1% | 0%
Discontinued due to adverse reactions | 9% | 6%
Discontinued due to other reasonsb | 15% | 10%

aSubjects achieved and maintained confirmed HIV-1 RNA less than 400 copies per mL (less than 50 copies per mL) through Week 48 (Roche AMPLICOR HIV-1 MONITOR Assay Version 1.5).

bIncludes consent withdrawn, lost to follow up, protocol violations, those with missing data, and other reasons.

Treatment response by viral load strata is shown in Table 18.

Table 18. Proportions of Responders Through Week 48 by Screening Viral Load (APV30002)
Screening Viral Load HIV-1 RNA | LEXIVA 1,400 mg q.d./; Ritonavir 200 mg q.d. |  | Nelfinavir; 1,250 mg b.i.d.
(copies/mL) | <400 copies/mL | n | <400 copies/mL | n
≤100,000 | 72% | 197 | 73% | 194
>100,000 | 66% | 125 | 64% | 133

Through 48 weeks of therapy, the median increases from baseline in CD4+ cell counts were 203 cells per mm^3 in the group receiving LEXIVA and 207 cells per mm^3 in the nelfinavir group.

14.2 Protease Inhibitor-Experienced Adult Trials

APV30003: A randomized, open-label, multicenter trial evaluated 2 different regimens of LEXIVA plus ritonavir (LEXIVA Tablets 700 mg twice daily plus ritonavir 100 mg twice daily or LEXIVA Tablets 1,400 mg once daily plus ritonavir 200 mg once daily) versus lopinavir/ritonavir (400 mg/100 mg twice daily) in 315 subjects who had experienced virologic failure to 1 or 2 prior protease inhibitor-containing regimens.

The mean age of the subjects in this trial was 42 years (range: 24 to 72 years); 85% were male, 33% were CDC Class C, 67% were Caucasian, 24% were black, and 9% were Hispanic. The median CD4+ cell count at baseline was 263 cells per mm^3 (range: 2 to 1,171 cells per mm^3). Baseline median plasma HIV-1 RNA level was 4.14 log10 copies per mL (range: 1.69 to 6.41 log10 copies per mL).

The median durations of prior exposure to NRTIs were 257 weeks for subjects receiving LEXIVA/ritonavir twice daily (79% had greater than or equal to 3 prior NRTIs) and 210 weeks for subjects receiving lopinavir/ritonavir (64% had greater than or equal to 3 prior NRTIs). The median durations of prior exposure to protease inhibitors were 149 weeks for subjects receiving LEXIVA/ritonavir twice daily (49% received greater than or equal to 2 prior protease inhibitors) and 130 weeks for subjects receiving lopinavir/ritonavir (40% received greater than or equal to 2 prior protease inhibitors).

The time-averaged changes in plasma HIV-1 RNA from baseline (AAUCMB) at 48 weeks (the endpoint on which the trial was powered) were -1.4 log10 copies per mL for twice-daily LEXIVA/ritonavir and -1.67 log10 copies per mL for the lopinavir/ritonavir group.

The proportions of subjects who achieved and maintained confirmed HIV-1 RNA less than 400 copies per mL (secondary efficacy endpoint) were 58% with twice-daily LEXIVA/ritonavir and 61% with lopinavir/ritonavir (95% CI for the difference: -16.6, 10.1). The proportions of subjects with HIV-1 RNA less than 50 copies per mL with twice-daily LEXIVA/ritonavir and with lopinavir/ritonavir were 46% and 50%, respectively (95% CI for the difference: -18.3, 8.9). The proportions of subjects who were virologic failures were 29% with twice-daily LEXIVA/ritonavir and 27% with lopinavir/ritonavir.

The frequency of discontinuations due to adverse events and other reasons, and deaths were similar between treatment arms.

Through 48 weeks of therapy, the median increases from baseline in CD4+ cell counts were 81 cells per mm^3 with twice-daily LEXIVA/ritonavir and 91 cells per mm^3 with lopinavir/ritonavir.

This trial was not large enough to reach a definitive conclusion that LEXIVA/ritonavir and lopinavir/ritonavir are clinically equivalent.

Once-daily administration of LEXIVA plus ritonavir is not recommended for protease inhibitor-experienced patients. Through Week 48, 50% and 37% of subjects receiving LEXIVA 1,400 mg plus ritonavir 200 mg once daily had plasma HIV-1 RNA less than 400 copies per mL and less than 50 copies per mL, respectively.

14.3 Pediatric Trials

Three open-label trials in pediatric subjects aged at least 4 weeks to 18 years were conducted. In one trial (APV29005), twice-daily dosing regimens (LEXIVA with or without ritonavir) were evaluated in combination with other antiretroviral agents in pediatric subjects aged 2 to 18 years. In a second trial (APV20002), twice-daily dosing regimens (LEXIVA with ritonavir) were evaluated in combination with other antiretroviral agents in pediatric subjects aged at least 4 weeks to less than 2 years. A third trial (APV20003) evaluated once-daily dosing of LEXIVA with ritonavir; the pharmacokinetic data from this trial did not support a once-daily dosing regimen in any pediatric patient population.

APV29005: LEXIVA: Twenty (18 therapy-naive and 2 therapy-experienced) pediatric subjects received LEXIVA Oral Suspension without ritonavir twice daily. At Week 24, 65% (13/20) achieved HIV-1 RNA less than 400 copies per mL, and the median increase from baseline in CD4+ cell count was 350 cells per mm^3.

LEXIVA plus Ritonavir: Forty-nine protease inhibitor-naive and 40 protease inhibitor-experienced pediatric subjects received LEXIVA Oral Suspension or Tablets with ritonavir twice daily. At Week 24, 71% of protease inhibitor-naive (35/49) and 55% of protease inhibitor-experienced (22/40) subjects achieved HIV-1 RNA less than 400 copies per mL; median increases from baseline in CD4+ cell counts were 184 cells per mm^3 and 150 cells per mm^3 in protease inhibitor-naive and experienced subjects, respectively.

APV20002: Fifty-four pediatric subjects (49 protease inhibitor-naive and 5 protease inhibitor-experienced) received LEXIVA Oral Suspension with ritonavir twice daily. At Week 24, 72% of subjects achieved HIV-1 RNA less than 400 copies per mL. The median increases from baseline in CD4+ cell counts were 400 cells per mm^3 in subjects aged at least 4 weeks to less than 6 months and 278 cells per mm^3 in subjects aged 6 months to 2 years.

16 HOW SUPPLIED/STORAGE AND HANDLING

LEXIVA Tablets, 700 mg, are pink, film-coated, capsule-shaped, biconvex tablets, with “GX LL7” debossed on one face.

They are supplied by State of Florida DOH Central Pharmacy as follows:

NDC | Strength | Quantity/Form | Color | Source Prod. Code
53808-1010-1 | 700 MG | 30 Tablets in a Blister Pack | PINK | 49702-207

Store at controlled room temperature of 25°C (77°F); excursions permitted to 15° to 30°C (59° to 86°F) (see USP Controlled Room Temperature).

17 PATIENT COUNSELING INFORMATION

See FDA-approved Patient Labeling (Patient Information)

17.1 Drug Interactions

A statement to patients and healthcare providers is included on the product’s bottle label: ALERT: Find out about medicines that should NOT be taken with LEXIVA.

LEXIVA may interact with many drugs; therefore, patients should be advised to report to their healthcare provider the use of any other prescription or nonprescription medication or herbal products, particularly St. John’s wort.

Patients receiving PDE5 inhibitors should be advised that they may be at an increased risk of PDE5 inhibitor-associated adverse events, including hypotension, visual changes, and priapism, and should promptly report any symptoms to their healthcare provider.

Patients receiving hormonal contraceptives should be instructed to use alternate contraceptive measures during therapy with LEXIVA because hormonal levels may be altered, and if used in combination with LEXIVA and ritonavir, liver enzyme elevations may occur.

17.2 Sulfa Allergy

Patients should inform their healthcare provider if they have a sulfa allergy. The potential for cross-sensitivity between drugs in the sulfonamide class and fosamprenavir is unknown.

17.3 Redistribution/Accumulation of Body Fat

Patients should be informed that redistribution or accumulation of body fat may occur in patients receiving antiretroviral therapy, including LEXIVA, and that the cause and long-term health effects of these conditions are not known at this time.

17.4 Information About Therapy With LEXIVA

LEXIVA is not a cure for HIV-1 infection and patients may continue to experience illnesses associated with HIV-1 infection, including opportunistic infections. Patients should remain under the care of a physician when using LEXIVA.

Patients should be advised to avoid doing things that can spread HIV-1 infection to others.

- Do not share needles or other injection equipment.
- Do not share personal items that can have blood or body fluids on them, like toothbrushes and razor blades.
- Do not have any kind of sex without protection. Always practice safe sex by using a latex or polyurethane condom to lower the chance of sexual contact with semen, vaginal secretions, or blood.
- Do not breastfeed. We do not know if LEXIVA can be passed to your baby in your breast milk and whether it could harm your baby. Also, mothers with HIV-1 should not breastfeed because HIV-1 can be passed to the baby in the breast milk.

Patients should be told that sustained decreases in plasma HIV-1 RNA have been associated with a reduced risk of progression to AIDS and death. Patients should be advised to take LEXIVA every day as prescribed. LEXIVA must always be used in combination with other antiretroviral drugs. Patients should not alter the dose or discontinue therapy without consulting their physician. If a dose is missed, patients should take the dose as soon as possible and then return to their normal schedule. However, if a dose is skipped, the patient should not double the next dose.

PATIENT INFORMATION

LEXIVA® (lex-EE-vah)

(fosamprenavir calcium)

Tablets

and

Oral Suspension

Important: LEXIVA can interact with other medicines and cause serious side effects. It is important to know the medicines that should not be taken with LEXIVA. See the section “Who should not take LEXIVA?”

Read this Patient Information before you start taking LEXIVA and each time you get a refill. There may be new information. This information does not take the place of talking with your healthcare provider about your medical condition or treatment.

What is LEXIVA?

LEXIVA is a prescription anti-HIV medicine used with other anti-HIV medicines to treat human immunodeficiency (HIV-1) infections in adults and children 4 weeks of age and older. LEXIVA is a type of anti-HIV medicine called a protease inhibitor. HIV-1 is the virus that causes AIDS (Acquired Immune Deficiency Syndrome).

When used with other anti-HIV medicines, LEXIVA may help:

1. Reduce the amount of HIV-1 in your blood. This is called “viral load”.
2. Increase the number of white blood cells called CD4 (T) cells, which help fight off other infections. Reducing the amount of HIV-1 and increasing the CD4 (T) cell count may improve your immune system. This may reduce your risk of death or infections that can happen when your immune system is weak (opportunistic infections).

It is not known if LEXIVA is safe and effective in children less than 4 weeks of age.

LEXIVA does not cure HIV-1 infection or AIDS. People taking LEXIVA may develop infections or other conditions associated with HIV-1 infection, including opportunistic infections (for example, pneumonia and herpes virus infections).

You should remain under the care of your healthcare provider when using LEXIVA.

Avoid doing things that can spread HIV-1 infection to others.

- Do not share needles or other injection equipment.
- Do not share personal items that can have blood or body fluids on them, like toothbrushes and razor blades.
- Do not have any kind of sex without protection. Always practice safe sex by using a latex or polyurethane condom to lower the chance of sexual contact with semen, vaginal secretions, or blood.

Ask your healthcare provider if you have any questions on how to prevent passing HIV to other people.

Who should not take LEXIVA?

Do not take LEXIVA if you take any of the following medicines:

- alfuzosin (UROXATRAL®)
- flecainide (TAMBOCOR™)
- propafenone (RYTHMOL SR®)
- rifampin (RIFADIN®, RIFAMATE®, RIFATER®, RIMACTANE®)
- ergot including:
  ∘ dihydroergotamine mesylate (D.H.E. 45®, MIGRANAL®)
  ∘ ergotamine tartrate (CAFERGOT®, MIGERGOT®, ERGOMAR®, MEDIHALER ERGOTAMINE®)
  ∘ methylergonovine (METHERGINE®)
- St. John’s wort (Hypericum perforatum)
- lovastatin (ADVICOR®, ALTOPREV®, MEVACOR®)
- simvastatin (ZOCOR®, VYTORIN®, SIMCOR®)
- pimozide (ORAP®)
- delavirdine mesylate (RESCRIPTOR®)
- sildenafil (REVATIO®), for treatment of pulmonary arterial hypertension
- triazolam (HALCION®)

Serious problems can happen if you or your child take any of the medicines listed above with LEXIVA.

Do not take LEXIVA if you are allergic to AGENERASE® (amprenavir), fosamprenavir calcium, or any of the ingredients in LEXIVA. See the end of this leaflet for a complete list of ingredients in LEXIVA.

What should I tell my healthcare provider before taking LEXIVA?

Before taking LEXIVA, tell your healthcare provider if you:

- are allergic to medicines that contain sulfa
- have liver problems, including hepatitis B or C
- have kidney problems
- have high blood sugar (diabetes)
- have hemophilia
- have any other medical condition
- are pregnant or plan to become pregnant. It is not known if LEXIVA will harm your unborn baby.

Pregnancy Registry. There is a pregnancy registry for women who take antiviral medicines during pregnancy. The purpose of the registry is to collect information about the health of you and your baby. Talk to your healthcare provider about how you can take part in this registry.

- Do not breastfeed. We do not know if LEXIVA can be passed to your baby in your breast milk and whether it could harm your baby. Also, mothers with HIV-1 should not breastfeed because HIV-1 can be passed to the baby in the breast milk.

Tell your healthcare provider about all prescription and non-prescription medicines you take. Also tell your healthcare provider about any vitamins, herbal supplements, and dietary supplements you are taking.

Taking LEXIVA with certain other medicines may cause serious side effects. LEXIVA may affect the way other medicines work, and other medicines may affect how LEXIVA works.

Especially tell your healthcare provider if you take estrogen-based contraceptives (birth control pills). LEXIVA may reduce effectiveness of estrogen-based contraceptives. During treatment with LEXIVA, you should use a different contraceptive method.

Know all the medicines that you take. Keep a list of them with you to show healthcare providers and pharmacists when you get a new medicine.

How should I take LEXIVA?

- Stay under the care of a healthcare provider while taking LEXIVA.
- Take LEXIVA exactly as prescribed by your healthcare provider.
- Do not change your dose or stop taking LEXIVA without talking with your healthcare provider.
- If your child is taking LEXIVA, your child’s healthcare provider will decide the right dose based on your child’s weight.
- You can take LEXIVA Tablets with or without food.
- Adults should take LEXIVA Oral Suspension without food.
- Children should take LEXIVA Oral Suspension with food. If your child vomits within 30 minutes after taking a dose of LEXIVA, the dose should be repeated.
- Shake LEXIVA Oral Suspension well before each use.
- If you miss a dose of LEXIVA, take the next dose as soon as possible and then take your next dose at the regular time. Do not double the next dose. If you take too much LEXIVA, call your healthcare provider or go to the nearest hospital emergency room right away.

What are the possible side effects of LEXIVA?

LEXIVA may cause serious side effects including:

- Severe skin rash. LEXIVA may cause severe or life-threatening skin reactions or rash.

If you get a rash with any of the following symptoms, stop taking LEXIVA and call your healthcare provider or get medical help right away:

  ∘ hives or sores in your mouth, or your skin blisters and peels
  ∘ trouble swallowing or breathing
  ∘ swelling of your face, eyes, lips, tongue, or throat
- Liver problems. Your healthcare provider should do blood tests before and during your treatment with LEXIVA to check your liver function. Some people with liver problems, including hepatitis B or C, may have an increased risk of developing worsening liver problem during treatment with LEXIVA.
- Diabetes and high blood sugar (hyperglycemia). Some people who take protease inhibitors, including LEXIVA, can get high blood sugar, develop diabetes, or your diabetes can get worse. Tell your healthcare provider if you notice an increase in thirst or urinate often while taking LEXIVA.
- Changes in your immune system (Immune Reconstitution Syndrome) can happen when you start taking HIV medicines. Your immune system may get stronger and begin to fight infections that have been hidden in your body for a long time. Call your healthcare provider right away if you start having new symptoms after starting your HIV medicine.
- Changes in body fat. These changes can happen in people who take antiretroviral therapy. The changes may include an increased amount of fat in the upper back and neck (“buffalo hump”), breast, and around the back, chest, and stomach area. Loss of fat from the legs, arms, and face may also happen. The exact cause and long-term health effects of these conditions are not known.
- Changes in blood tests. Some people have changes in blood tests while taking LEXIVA. These include increases seen in liver function tests, blood fat levels, and decreases in white blood cells. Your healthcare provider should do regular blood tests before and during your treatment with LEXIVA.
- Increased bleeding problems in some people with hemophilia. Some people with hemophilia have increased bleeding with protease inhibitors, including LEXIVA.
- Kidney stones. Some people have developed kidney stones while taking LEXIVA. Tell your healthcare provider right away if you develop signs or symptoms of kidney stones:
  ∘ pain in your side
  ∘ blood in your urine
  ∘ pain when you urinate

The most common side effects of LEXIVA in adults include:

- nausea
- vomiting
- diarrhea
- headache

Vomiting is the most common side effect in children when taking LEXIVA.

Tell your healthcare provider about any side effect that bothers you or that does not go away.

These are not all the possible side effects of LEXIVA. For more information, ask your healthcare provider or pharmacist.

Call your doctor for medical advice about side effects. You may report side effects to FDA at 1-800-FDA-1088.

How should I store LEXIVA?

- Store LEXIVA Tablets at room temperature between 68°F to 77°F (20°C to 25°C).
- Keep the bottle of LEXIVA Tablets tightly closed.
- Store LEXIVA Oral Suspension between 41°F to 86°F (5°C to 30°C). Refrigeration of LEXIVA Oral Suspension may improve taste for some people.
- Do not freeze.
  Keep LEXIVA and all medicines out of the reach of children.

General information about LEXIVA

Medicines are sometimes prescribed for purposes other than those listed in a Patient Information leaflet. Do not use LEXIVA for a condition for which it was not prescribed. Do not give LEXIVA to other people, even if they have the same symptoms you have. It may harm them.

This leaflet summarizes the most important information about LEXIVA. If you would like more information, talk with your healthcare provider. You can ask your pharmacist or healthcare provider for information about LEXIVA that is written for health professionals.

For more information call 877-844-8872 or go to www.LEXIVA.com.

What are the ingredients in LEXIVA?

Tablets:

Active ingredient: fosamprenavir calcium

Inactive ingredients: colloidal silicon dioxide, croscarmellose sodium, magnesium stearate, microcrystalline cellulose, and povidone K30. The tablet film-coating contains the inactive ingredients hypromellose, iron oxide red, titanium dioxide, and triacetin.

Oral Suspension:

Active ingredient: fosamprenavir calcium

Inactive ingredients: artificial grape-bubblegum flavor, calcium chloride dihydrate, hypromellose, methylparaben, natural peppermint flavor, polysorbate 80, propylene glycol, propylparaben, purified water, and sucralose.

This Patient Information has been approved by the U.S. Food and Drug Administration.

LEXIVA and AGENERASE are registered trademarks of ViiV Healthcare.

The brands listed are trademarks of their respective owners and are not trademarks of ViiV Healthcare. The makers of these brands are not affiliated with and do not endorse ViiV Healthcare or its products.

Manufactured for:

ViiV Healthcare

Research Triangle Park, NC 27709

Vertex Pharmaceuticals Incorporated

Cambridge, MA 02139

by:

GlaxoSmithKline

Research Triangle Park, NC 27709

This Product was Repackaged By:

State of Florida DOH Central Pharmacy
104-2 Hamilton Park Drive
Tallahassee, FL 32304
USA

PACKAGE LABEL

Label Image for 53808-1010
700mg